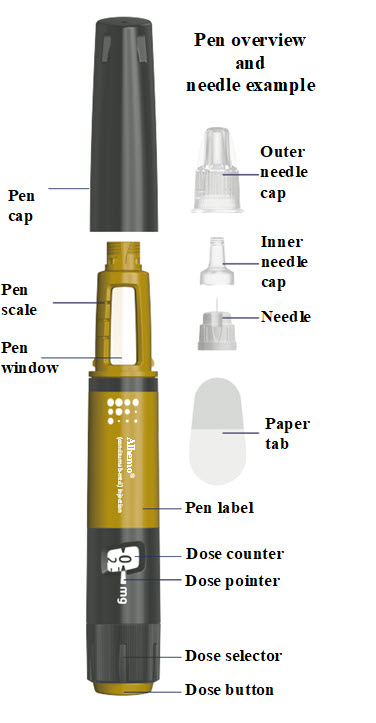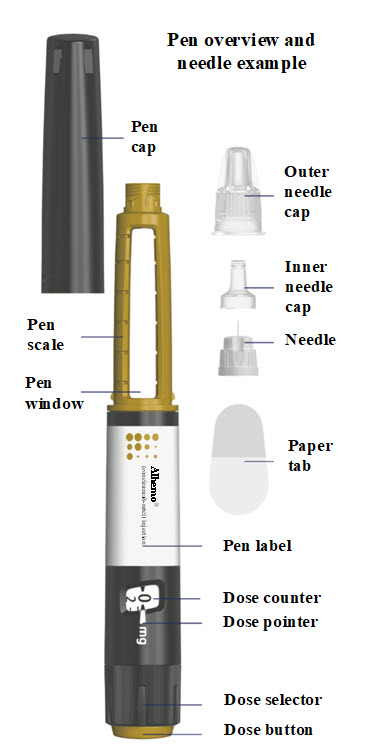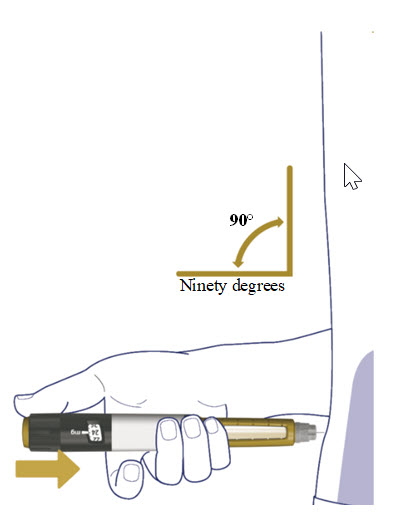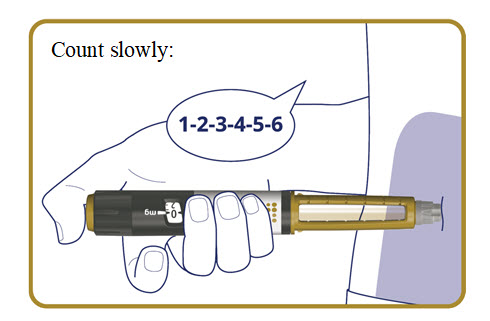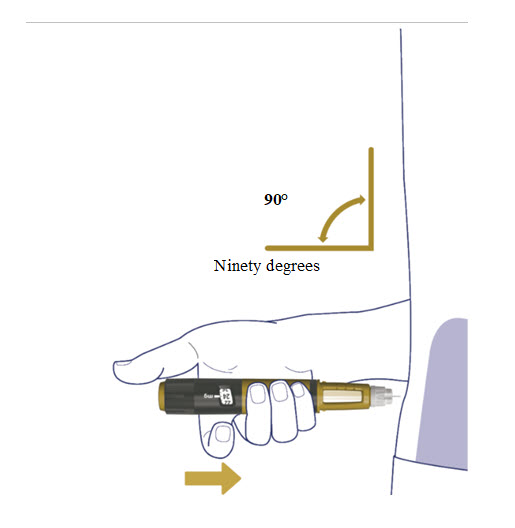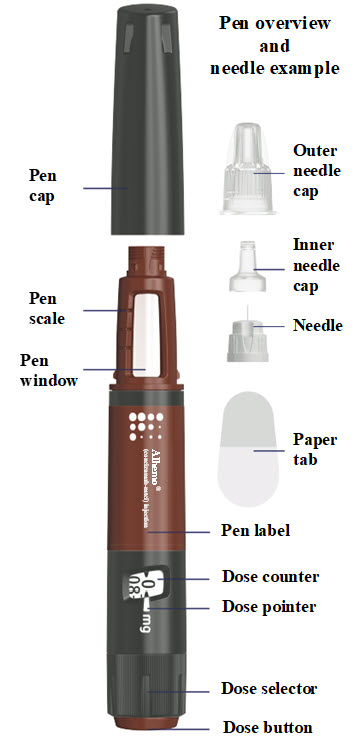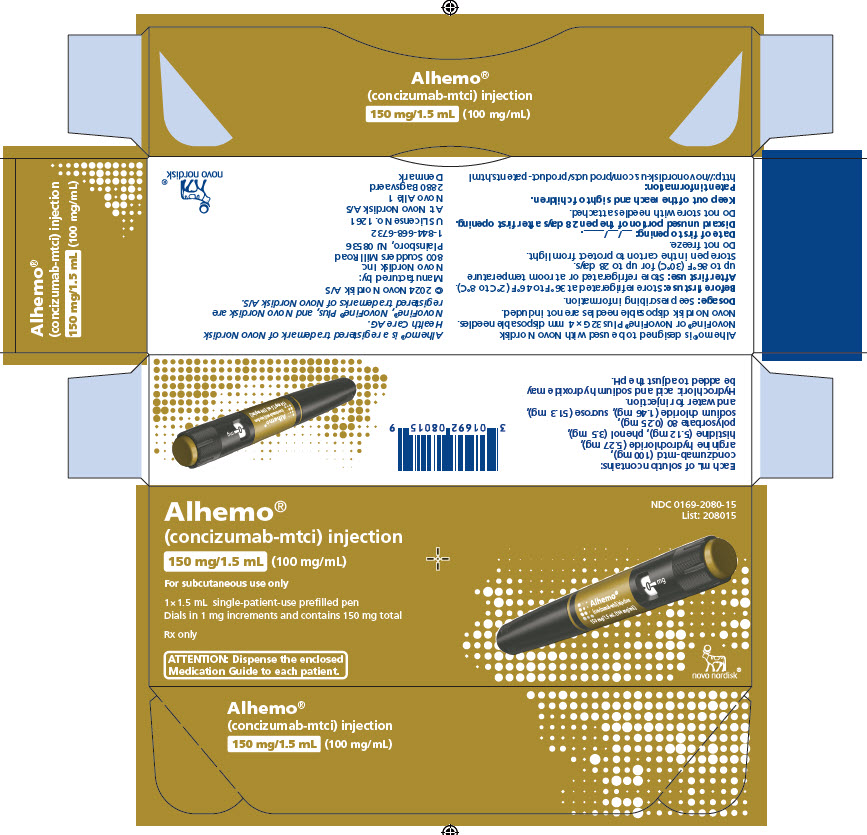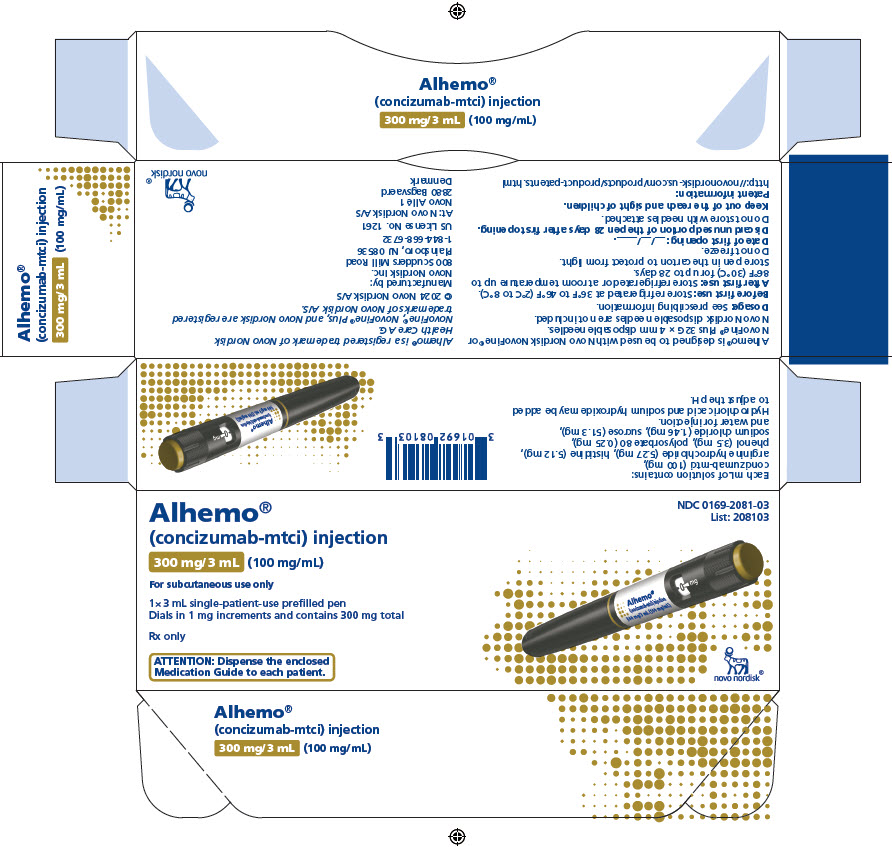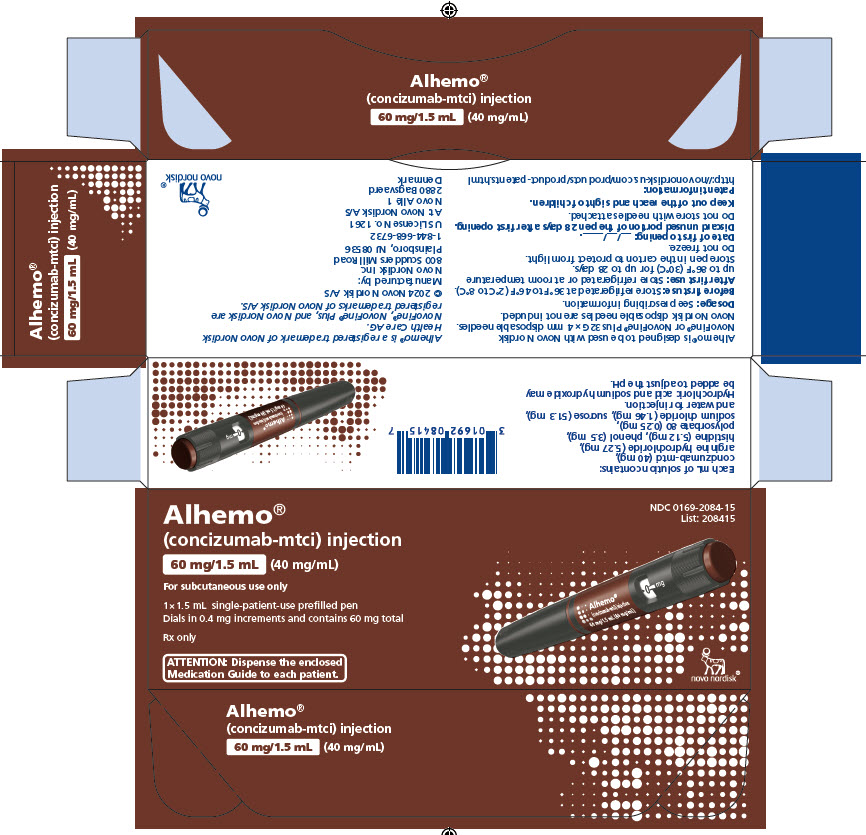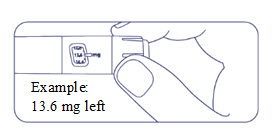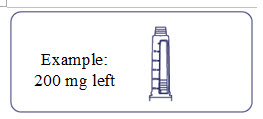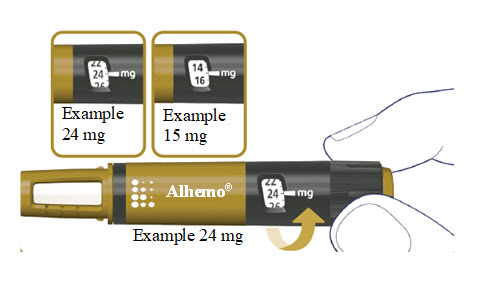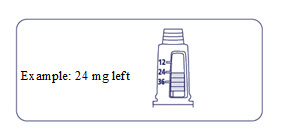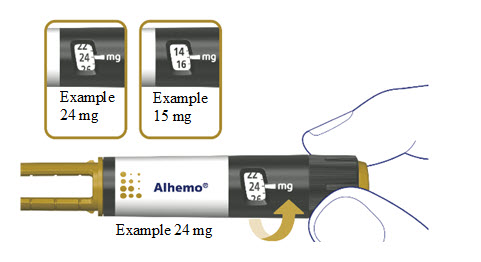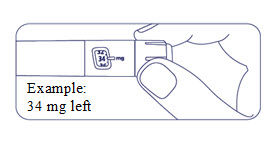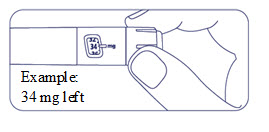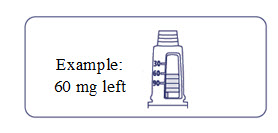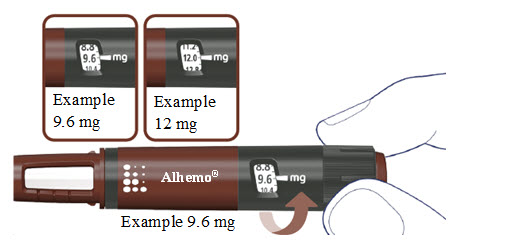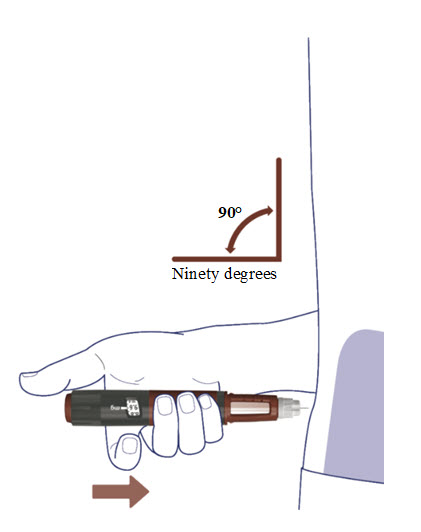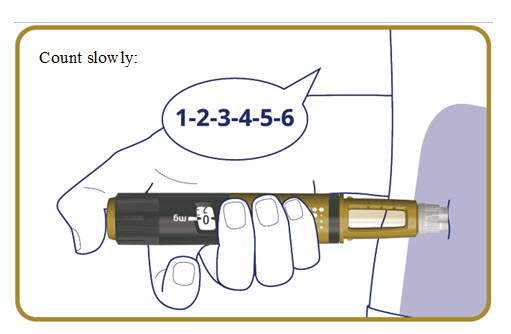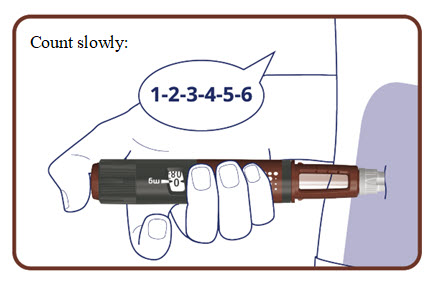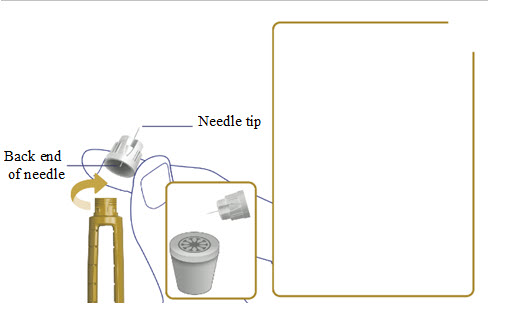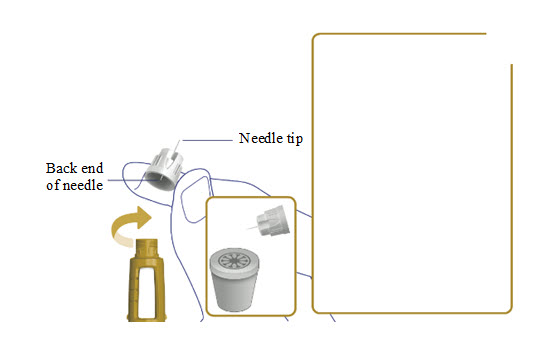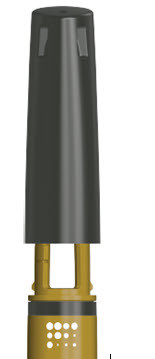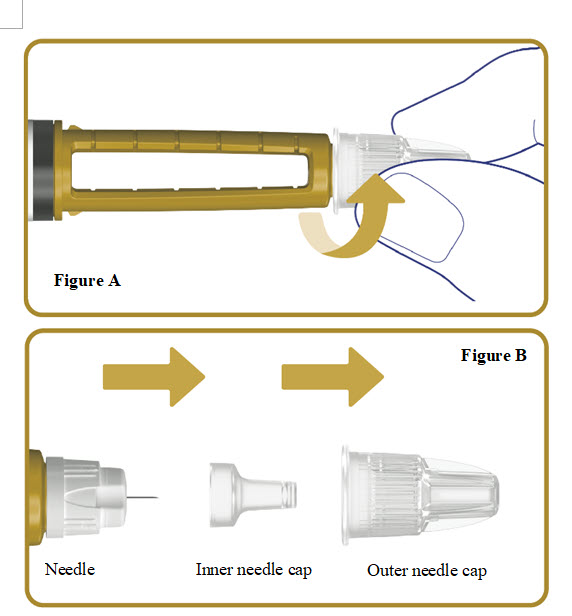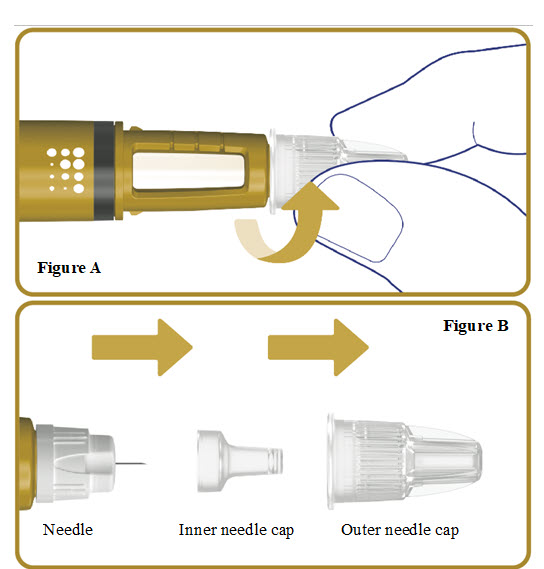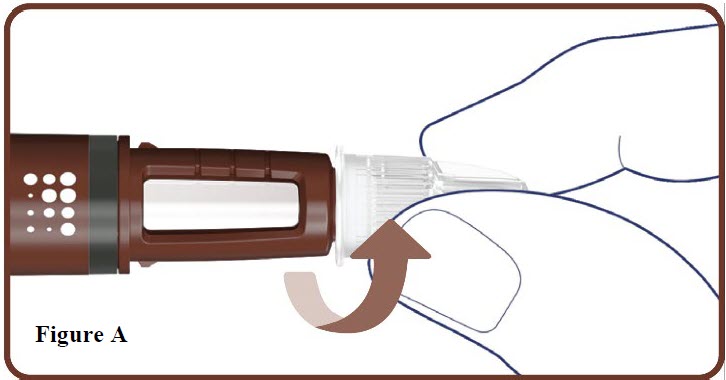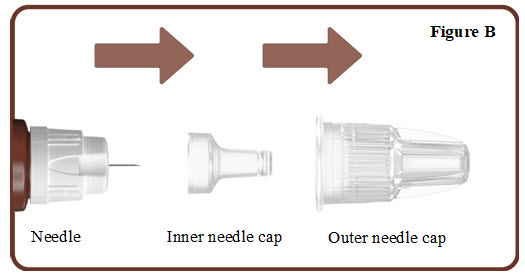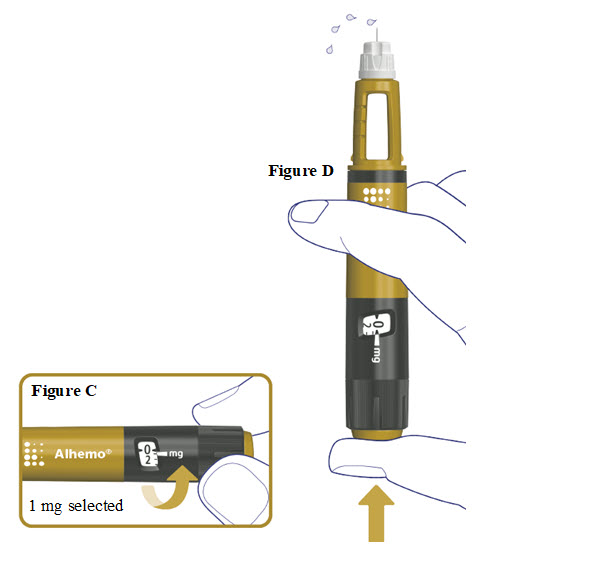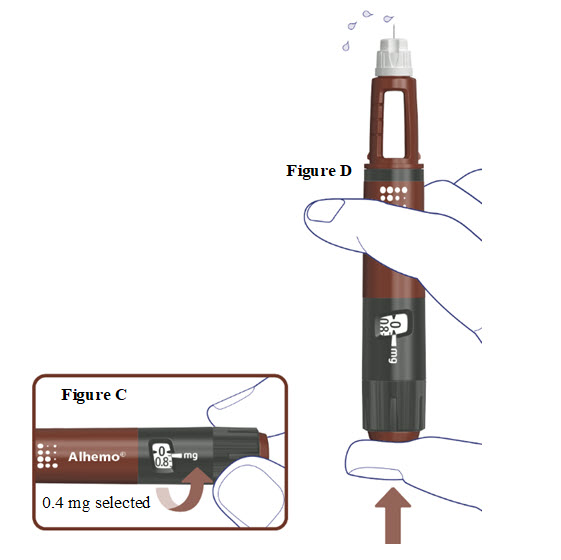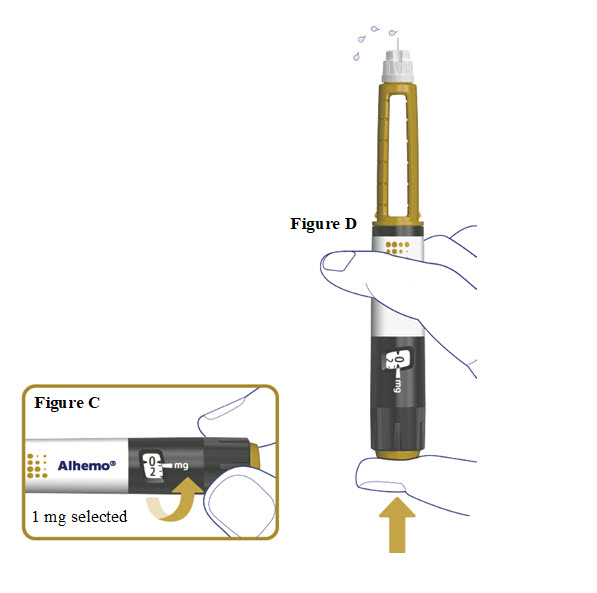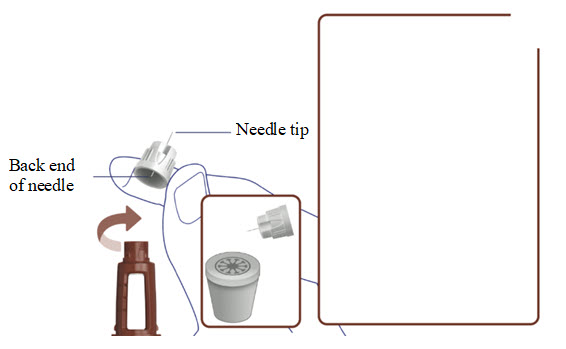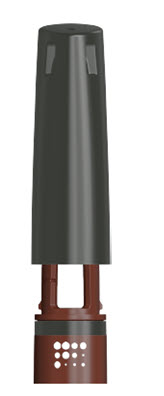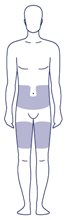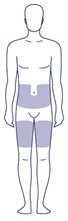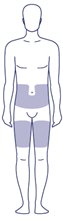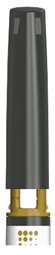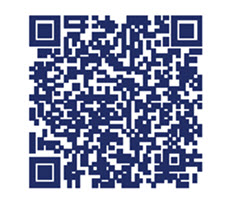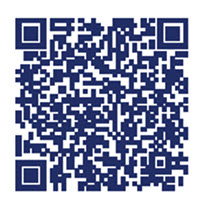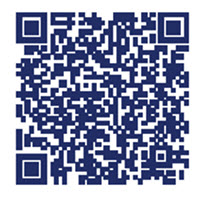 DRUG LABEL: Alhemo
NDC: 0169-2084 | Form: INJECTION, SOLUTION
Manufacturer: Novo Nordisk
Category: prescription | Type: HUMAN PRESCRIPTION DRUG LABEL
Date: 20250701

ACTIVE INGREDIENTS: CONCIZUMAB 40 mg/1 mL
INACTIVE INGREDIENTS: ARGININE 5.27 mg/1 mL; HISTIDINE 5.12 mg/1 mL; PHENOL 3.5 mg/1 mL; POLYSORBATE 80 0.25 mg/1 mL; SODIUM CHLORIDE 1.46 mg/1 mL; SUCROSE 51.3 mg/1 mL; WATER

HIGHLIGHTS OF PRESCRIBING INFORMATION

These highlights do not include all the information needed to use Alhemo safely and effectively. See full prescribing information for Alhemo.
Alhemo® (concizumab-mtci) injection, for subcutaneous use
Initial U.S. Approval: 2024

1 INDICATIONS AND USAGE

Alhemo is a tissue factor pathway inhibitor (TFPI) antagonist indicated for routine prophylaxis to prevent or reduce the frequency of bleeding episodes in adult and pediatric patients 12 years of age and older with:

- hemophilia A (congenital factor VIII deficiency) with or without FVIII inhibitors
- hemophilia B (congenital factor IX deficiency) with or without FIX inhibitors (1)

2 DOSAGE AND ADMINISTRATION

Administer Alhemo by subcutaneous injection to the abdomen or thigh with daily rotation of injection sites. (2.2)

Recommended dosing regimen:

- Day 1: Loading dose of 1 mg/kg
- Day 2: Once daily dose of 0.2 mg/kg until individualization of maintenance dose (2.1)
  - 4 weeks after initiation of treatment: For dose optimization, measure concizumab‑mtci plasma concentration by Concizumab Enzyme-Linked Immunosorbent Assay (ELISA) prior to administration of next scheduled dose using an FDA-authorized test for the measurement of concizumab-mtci concentration in plasma.

See full Prescribing Information for important preparation and administration instructions and dosage adjustment. (2.1, 2.3, 2.4)

3 DOSAGE FORMS AND STRENGTHS

Injection:

- 60 mg/1.5 mL (40 mg/mL) in a single-patient-use prefilled pen (3)
- 150 mg/1.5 mL (100 mg/mL) in a single-patient-use prefilled pen (3)
- 300 mg/3 mL (100 mg/mL) in a single-patient-use prefilled pen (3)

4 CONTRAINDICATIONS

Alhemo is contraindicated in patients with a history of known serious hypersensitivity to Alhemo or its components or the inactive ingredients. (4)

5 WARNINGS AND PRECAUTIONS

- Thromboembolic Events: Monitor patients for thromboembolic events. Advise patients to report signs and symptoms, and if they occur discontinue prophylaxis. (5.1)
- Hypersensitivity Reactions: In the event of a severe hypersensitivity reaction, discontinue Alhemo. (5.2)
- Increased Laboratory Values of Fibrin D dimer and Prothrombin Fragment 1.2: Alhemo increases values of fibrin D dimer and prothrombin fragment 1.2. (5.3)

6 ADVERSE REACTIONS

The most frequently reported adverse reactions (incidence ≥5%) were injection site reactions, headache and urticaria. (6.1)

To report SUSPECTED ADVERSE REACTIONS, contact Novo Nordisk Inc. at 1-800-727-6500 or FDA at 1-800-FDA-1088 or www.fda.gov/medwatch.

7 DRUG INTERACTIONS

Breakthrough Bleeding Treatment: While treatment with all bypassing agents (e.g., rFVIIa or aPCC) can be used for breakthrough bleeds, high and/or frequent doses of FVIII, FIX, or bypassing agents with Alhemo increases the risk of thromboembolism. (7.1)

FULL PRESCRIBING INFORMATION

1 INDICATIONS AND USAGE

Alhemo is indicated for routine prophylaxis to prevent or reduce the frequency of bleeding episodes in adult and pediatric patients 12 years of age and older with:

- hemophilia A (congenital factor VIII deficiency) with or without FVIII inhibitors
- hemophilia B (congenital factor IX deficiency) with or without FIX inhibitors

2 DOSAGE AND ADMINISTRATION

2.1 Recommended Dosage

For subcutaneous use only.

Alhemo should be administered once daily. Avoid missed doses.

Recommended dosing regimen:

- Day 1: Loading dose of 1 mg/kg
- Day 2: Once daily dose of 0.2 mg/kg until individualization of maintenance dose (see below)
- 4 weeks after initiation of treatment: For dose optimization measure concizumab-mtci plasma concentration by Concizumab Enzyme-Linked Immunosorbent Assay (ELISA) prior to administration of next scheduled dose using an FDA-authorized test. Information on the FDA-authorized test for the measurement of concizumab-mtci plasma concentration is available at https://www.accessdata.fda.gov/scripts/cdrh/cfdocs/cfpmn/denovo.cfm. Once the concizumab-mtci concentration result is available, individualize the maintenance dose of Alhemo no later than 8 weeks after initiation of treatment, based on the following concizumab-mtci plasma concentrations:
- Less than 200 ng/mL: adjust to a once daily dose of 0.25 mg/kg
- 200 to 4,000 ng/mL: continue once daily dose of 0.2 mg/kg
- Greater than 4,000 ng/mL: adjust to a once daily dose of 0.15 mg/kg

The calculated dose is rounded off to the nearest injectable dose as follows:

- 60 mg/1.5 mL (40 mg/mL) in increments of 0.4 mg (brown label)
- 150 mg/1.5 mL (100 mg/mL) in increments of 1 mg (gold label)
- 300 mg/3 mL (100 mg/mL) in increments of 1 mg (white label)

Additional measurements of concizumab-mtci plasma concentration should be taken at routine clinical follow-ups provided the patient has been on the same maintenance dose for 8 weeks of treatment to ensure steady state plasma concentration. Maintenance of concizumab plasma concentration above 200 ng/mL is important to decrease the risk of bleeding episodes. If concizumab-mtci plasma concentration remains below 200 ng/mL at two consecutive measurements, evaluate the benefits of continued Alhemo treatment versus the potential risk of bleeding events, and consider alternative therapies if available.

As Alhemo is dosed by body weight (mg/kg), it is important to recalculate the dose when patients experience body weight changes.

Missed Dose

Adherence to daily dosing of Alhemo is important to maintain protection against bleeding. This is especially important during the initial 4 weeks of treatment to ensure a correct maintenance dose is established. Patients who miss a dose during the initial 4-week period should inform their healthcare professional and resume once daily dosing at the initial 0.2 mg/kg dose level.

Missed Doses Once the Maintenance Dose Has Been Established

The following dosing guidelines should apply ONLY when a patient has forgotten to or neglected to take their once daily maintenance dose:

- 1 missed dose: Resume once daily treatment at the maintenance dose level
- 2 to 6 missed doses: Resume treatment with a double dose followed by once daily treatment at the maintenance dose level
- 7 or more missed doses: Physician should be contacted, and a new loading dose should be considered [see Dosage and Administration (2.1)]

Management of Breakthrough Bleeds

No dose adjustment of Alhemo is required in the case of breakthrough bleeds.

Management in the Perioperative Setting

No dose adjustment of Alhemo is required in the case of minor surgeries.

As there is limited experience in the perioperative setting, it is generally recommended to pause Alhemo at least 4 days prior to major surgery. Alhemo therapy can be resumed 10-14 days after surgery on the same maintenance dose without a new loading dose, considering the overall clinical picture of the patient. If necessary, consult a physician experienced in surgery of patients with bleeding disorders.

Immune Tolerance Induction

The safety and efficacy of concomitant use of Alhemo in patients receiving ongoing Immune Tolerance Induction (ITI), a desensitization strategy for the eradication of inhibitors, have not been established, and no data are available. Careful assessment of the potential benefits and risks should be performed if continuation or initiation of Alhemo during ITI is considered.

2.2 Changing to Alhemo from Other Hemostatic Products

- Discontinue treatment with rFVIIa at least 12 hours before starting Alhemo.
- Discontinue treatment with activated prothrombin complex concentrate (aPCC) at least 48 hours before starting Alhemo.
- Discontinue prophylactic use of standard half-life factor VIII (FVIII) or factor IX (FIX) at least 24 hours before starting Alhemo.
- When changing from other products to Alhemo, the half-life of the previous product should be considered.

Healthcare providers should discuss with patients receiving Alhemo and/or their caregivers the dose and schedule of bypassing agents or FVIII or FIX, if required, while receiving Alhemo prophylaxis.

2.3 Instructions and Dosage Modification for Breakthrough Bleeding

Treatment with FVIII or FIX or all bypassing agents (e.g., rFVIIa or aPCC) can be used for breakthrough bleeds, and the dose and duration will depend on the location and severity of the bleed.

For mild and moderate bleeds that require additional treatment with FVIII or FIX or bypassing agents (e.g., rFVIIa or aPCC), the lowest-approved dose and the dose interval in the approved product labeling is recommended. For aPCC, a maximum dose of 100 units/kg body weight within 24 hours is recommended.

For severe bleeds, follow the dosing instructions provided in the approved labeling for the specific product based on clinical judgement.

2.4 Administration and Use Instructions

Treatment is intended for use under the guidance of a healthcare provider. Treatment should be initiated in a nonbleeding state.

Alhemo may be self-administered or administered by a caregiver after appropriate training and reading the Instructions for Use, if a healthcare provider determines that is appropriate.

Administer Alhemo by subcutaneous injection to the abdomen or thigh with rotation of injection site every day. Subcutaneous injections should not be given in areas where the skin is tender, bruised, red or hard, or areas where there are moles, scars, or stretch marks. Children and lean patients should be instructed to use injection techniques that minimize risk of intramuscular injection, e.g. injecting into a pinched fold of skin.

Always use a new needle for each injection.

Parenteral drug products should be inspected visually for particulate matter and discoloration prior to administration, whenever solution and container permit. Alhemo is a clear to slightly opalescent and colorless to slightly yellow solution that may contain translucent to white particles. Do not use if the solution is discolored.

Each Alhemo prefilled pen is for use by a single patient. An Alhemo pen must not be shared between patients, even if the needle is changed.

Alhemo is recommended to be used with NovoFine® or NovoFine® Plus needles with a gauge of 32 and a length of 4 mm. If needles longer than 4 mm are used, injection techniques that minimize the risk of intramuscular injection should be used.

Instructions for delivering the dosage are provided in the Instructions for Use leaflet enclosed with each Alhemo single-patient-use prefilled pen.

3 DOSAGE FORMS AND STRENGTHS

Alhemo injection is a clear to slightly opalescent and colorless to slightly yellow solution that may contain translucent to white particles, available in the following presentations:

- 60 mg/1.5 mL (40 mg/mL) in a single-patient-use prefilled pen
- 150 mg/1.5 mL (100 mg/mL) in a single-patient-use prefilled pen
- 300 mg/3 mL (100 mg/mL) in a single-patient-use prefilled pen

4 CONTRAINDICATIONS

Alhemo is contraindicated in patients with a history of known serious hypersensitivity to Alhemo or its components or the inactive ingredients [see Warnings and Precautions (5.1)and Description (11)].

5 WARNINGS AND PRECAUTIONS

5.1 Thromboembolic Events

Alhemo may cause thromboembolic events. Venous and arterial thromboembolic events were reported in 1.9% of patients (6/320) in Alhemo clinical trials. These cases occurred in patients with multiple risk factors for thromboembolism, including the use of high doses or prolonged treatment with factor product or bypassing agent (2 of 6 patients).

Risk factors for thromboembolism may include the use of high and/or frequent doses of breakthrough bleed treatments (factor products or bypassing agents) or conditions in which tissue factor is overexpressed (e.g., atherosclerotic disease, crush injury, cancer, disseminated intravascular coagulation, thrombotic microangiopathy, or septicemia).

Inform Alhemo treated patients of signs and symptoms of thromboembolic events. Monitor patients for thromboembolic events. In case of suspicion of thromboembolic events, discontinue Alhemo and initiate further investigations and management strategies.

5.2 Hypersensitivity Reactions

Alhemo can cause hypersensitivity reaction, including serious cases. Alhemo is contraindicated in patients with a history of known serious hypersensitivity to Alhemo or its components or the inactive ingredients. Hypersensitivity reactions including erythema, rash, pruritus, and abdominal pain have occurred in Alhemo treated patients. One patient (less than 1% of patients treated in the clinical studies) experienced anaphylaxis which resolved after treatment with antihistamines and corticosteroids. Instruct patients of the signs of acute hypersensitivity reactions. Instruct patients to contact their healthcare provider for mild reactions and to seek urgent medical attention for moderate to severe reactions. Discontinue Alhemo if severe hypersensitivity symptoms occur and initiate medical management.

5.3 Increased Laboratory Values of Fibrin D-dimer and Prothrombin Fragment 1.2

Alhemo can cause increased levels of fibrin D-dimer and prothrombin fragment 1.2. Increased levels of fibrin D-dimer and increased levels of prothrombin fragment 1.2 were seen in 29 (9.1%) and 26 (8.1%) of patients, respectively. The plasma concentration of concizumab-mtci is positively correlated with fibrin D-dimer and prothrombin fragments 1.2 indicating a hemostatic effect of concizumab-mtci. For patients taking Alhemo, these coagulation biomarkers may not be reliable predictive markers for clinical decision-making with suspicion of thrombosis such as deep vein thrombosis (DVT) and pulmonary embolism (PE).

6 ADVERSE REACTIONS

The following clinically significant adverse reactions are discussed in greater detail in other sections of the labeling:

- Thromboembolic Events [see Warnings and Precautions (5.1)]
- Hypersensitivity Reactions [see Warnings and Precautions (5.2)]
- Increased Laboratory Values of Fibrin D-dimer and Prothrombin Fragment 1.2 [see Warnings and Precautions (5.3)]

6.1 Clinical Trials Experience

Because clinical trials are conducted under widely varying conditions, adverse reaction rates observed in the clinical trials of a drug cannot be directly compared to rates in clinical trials of another drug and may not reflect the rates observed in clinical practice.

The data in the WARNINGS AND PRECAUTIONS reflect exposure to Alhemo based on pooled data from clinical trials explorer3 (phase 1b), explorer4 (phase 2), explorer5 (phase 2), explorer7 (phase 3) and explorer8 (phase 3), in which a total of 320 male patients with hemophilia A with and without inhibitors and hemophilia B with and without inhibitors received at least one dose of Alhemo as routine prophylaxis. The patients were exposed for a total of 475 exposure years. Patients with HAwI (hemophilia A with inhibitors) and HBwI (hemophilia B with inhibitors)

The data described below reflect exposure of 52 patients with HAwI and HBwI who were previously treated on-demand therapy and

who were randomized in explorer7 to arm 1 to receive on- demand treatment with bypassing agents (n = 19) or arm 2 to receive

Alhemo prophylaxis (n = 33) at the recommended dosing regimen [see Clinical Studies (14.1)]. The median duration of treatment was

31.1 weeks (range 3.9, 72.9 weeks) in arm 1 (on-demand arm) and 40.1 weeks (range 3.1, 56.3 weeks) in arm 2 (Alhemo

prophylaxis).

Serious adverse reactions were reported in 6.1% of patients who received Alhemo. These serious adverse reactions were renal infarct

and hypersensitivity reaction. Permanent discontinuation of Alhemo due to an adverse reaction occurred in 1 patient due to a renal

infarct. Dosage interruptions of Alhemo due to an adverse reaction occurred in 1 patient (3%) and was a hypersensitivity reaction. The

most common adverse reactions (≥5%) were injection site reactions and urticaria (see Table 1).

Table 1. Adverse Reactions Reported in ≥5% HAwI and HBwI Patients Randomized to Alhemo in Explorer7

Adverse Reaction | Alhemo Prophylaxis; N=33; (%) | On-demand Treatment; N=19; (%)
Injection site reactions | 18% | 0%
Urticaria | 6% | 0%

Injection site reactions included: Injection site bruising, Injection site erythema, Injection site hematoma, Injection site hemorrhage, Injection site reaction and Injection site urticaria.

Urticaria included: Urticaria and Injection site urticaria.

Patients with HA (hemophilia A without inhibitors) and HB (hemophilia B without inhibitors)

The data described below reflect exposure of 63 patients with HA and HB who were previously treated on-demand therapy and who were randomized in explorer8 to arm 1 to receive on- demand treatment with factor product (n = 21) or arm 2 to receive Alhemo prophylaxis (n = 42) at the recommended dosing regimen [see Clinical Studies (14.2)]. The median duration of treatment was 24.1 weeks (range 23.6, 56.1 weeks) in arm 1 (on- demand arm) and 32.1 weeks (range 3.9, 33.6 weeks) in arm 2 (Alhemo prophylaxis).

The most common adverse reactions (≥5%) were injection site reactions and headache (see Table 2).

Table 2. Adverse Reactions Reported in ≥5% HA and HB Patients Randomized to Alhemo in Explorer8

Adverse Reaction | Alhemo Prophylaxis; N=42; (%) | On-demand Treatment; N=21; (%)
Injection site reactions | 7% | 0%
Headache | 7% | 0%

Injection site reactions included: injection site reaction, injection site rash, and injection site nodule

7 DRUG INTERACTIONS

7.1 Breakthrough Bleeding Treatment

Take appropriate precautions when treating breakthrough bleeding events in hemophilia patients receiving Alhemo prophylaxis and FVIII or FIX or a bypassing agent [see Dosage and Administration (2.1)]. For mild and moderate bleeds that require additional treatment with FVIII or FIX or bypassing agents (e.g., rFVIIa or aPCC), the lowest-approved dose in the approved product labeling is recommended. For aPCC, a maximum dose of 100 units/kg body weight within 24 hours is recommended. For severe bleeds, follow the dosing instructions provided in the approved labeling for the specific product based on clinical judgement.

Additive and sometimes synergistic increase in thrombin peak as quantified in the thrombin generation assay has been observed in plasma from hemophilia patients who were on prophylactic treatment with concizumab-mtci with concomitant presence of rFVIII, rFIX or bypassing agents including rFVIIa and aPCC [see Clinical Pharmacology (12.2)].

8 USE IN SPECIFIC POPULATIONS

8.1 Pregnancy

Risk Summary

Based on its mechanism of action, Alhemo may cause fetal harm when administered to a pregnant woman [see Clinical Pharmacology (12.1)]. There are no available data on Alhemo use in pregnant women to evaluate for a drug-associated risk of major birth defects, miscarriage or other adverse maternal or fetal outcomes. Animal reproduction studies have not been conducted with Alhemo. Although there are no data on concizumab-mtci, monoclonal antibodies can be actively transported across the placenta, and concizumab-mtci may cause fetal harm. It is unknown whether Alhemo can affect reproductive capacity. Alhemo should only be used during pregnancy if the potential benefit for the mother outweighs the potential risk to the fetus.

The estimated background risk of birth defects and miscarriage for the indicated population is unknown. All pregnancies have a background risk of birth defect, loss, or other adverse outcomes. In the U.S. general population, the estimated background risk of major birth defect and miscarriage in clinically recognized pregnancies is 2 to 4% and 15 to 20%, respectively.

8.2 Lactation

Risk Summary

There is no information regarding the presence of Alhemo in either human or animal milk, the effect on the breastfed child, or the effects on milk production.

Clinical Considerations

Human IgGs are known to be excreted in breast milk during the first few days after birth, decreasing to low concentrations soon afterwards; consequently, a risk to the breast-fed infant cannot be excluded during this short period. Afterwards, Alhemo could be used during breast-feeding if clinically needed.

8.3 Females and Males of Reproductive Potential

Pregnancy Testing
Pregnancy testing is recommended for females of reproductive potential.

Contraception

Women of childbearing potential should use a highly effective form of contraception during treatment with Alhemo and for 7 weeks after ending treatment. The benefits and thromboembolic risks of the type of contraceptives used should be evaluated by the treating physician.

8.4 Pediatric Use

The safety and effectiveness of Alhemo for hemophilia A and B with and without inhibitors have been established in pediatric patients aged 12 years and older. Use of Alhemo for this indication is supported by evidence from adequate and well-controlled studies in adult and pediatric patients aged 12 years and older [see Adverse Reactions (6.1) and Clinical Studies (14)]. The safety and effectiveness of Alhemo for hemophilia A and B with and without inhibitors have not been established in pediatric patients younger than 12 years of age.

8.5 Geriatric Use

Clinical studies of Alhemo did not include sufficient numbers of patients 65 years of age and older to determine whether they respond differently from younger adult patients.

8.6 Body Weight

The exposure of concizumab-mtci increased with increasing body weight [see Clinical Pharmacology (12.3)]. However, patients should receive the approved recommended Alhemo dosage titration and concizumab-mtci plasma concentration monitoring regardless of body weight [see Dosage and Administration (2.1)].

11 DESCRIPTION

Concizumab-mtci, is a humanized IgG4 monoclonal antibody produced by recombinant DNA technology in Chinese Hamster Ovary (CHO) cells with an approximate molecular weight of 149 kDa.

Alhemo (concizumab-mtci) injection is a clear to slightly opalescent, and colorless to slightly yellow solution that may contain translucent to white particles. Alhemo is supplied as a single-patient-use prefilled pen for subcutaneous injection.

Each 1 mL of Alhemo single-patient-use prefilled pen (60 mg/1.5 mL) contains 40 mg active ingredient concizumab-mtci. Each 1 mL of Alhemo single-patient-use prefilled pen (150 mg/1.5 mL) contains 100 mg active ingredient concizumab-mtci. Each 1 mL of Alhemo single-patient-use prefilled pen (300 mg/3 mL) contains 100 mg active ingredient concizumab-mtci.

Each 1 mL of Alhemo single-patient-use prefilled pen contains the following excipients: arginine hydrochloride (5.27 mg), histidine (5.12 mg), phenol (3.5 mg), polysorbate 80 (0.25 mg), sodium chloride (1.46 mg), sucrose (51.3 mg), and water for injection. Hydrochloric acid and sodium hydroxide may be added to adjust the pH to 6.0.

12 CLINICAL PHARMACOLOGY

12.1 Mechanism of Action

Concizumab-mtci is a monoclonal antibody antagonist of endogenous Tissue Factor Pathway Inhibitor (TFPI). Through the inhibition of TFPI, concizumab-mtci acts to enhance FXa production during the initiation phase of coagulation which leads to improved thrombin generation and clot formation with the goal of achieving hemostasis in patients with Hemophilia A or B regardless of their inhibitor status.

The effect of concizumab-mtci is not influenced by the presence of inhibitory antibodies to FVIII or FIX. There is no structural relationship or sequence homology between concizumab-mtci and FVIII or FIX and, as such, treatment with concizumab-mtci does not induce or enhance the development of direct inhibitors to FVIII or FIX.

12.2 Pharmacodynamics

Increasing concizumab-mtci dose levels resulted in decreased levels of free TFPI (plasma TFPI not bound to concizumab-mtci) and increased duration of free TFPI suppression. In hemophilia patients with inhibitors, free TFPI plasma levels predose decreased from a geometric mean (CV%) of 88.3 (20%) ng/mL at baseline to 10.7 (105%) ng/mL at week 24 in patients on Alhemo prophylaxis, while the geometric mean (CV%) was 76 (18%) ng/mL at week 24 for patients treated on-demand. In hemophilia patients without inhibitors, free TFPI plasma levels predose decreased from a geometric mean (CV%) of 84.2 (19%) ng/mL at baseline to 11.1 (102%) ng/mL at week 24 in patients on Alhemo prophylaxis, while the geometric mean (CV%) was 80.6 (18%) ng/mL at week 24 for patients treated on-demand. Mean thrombin peak within the range of normal plasma reflected that concizumab‑mtci re‐established thrombin generation capacity.

Drug Interaction

In vitro studies

Additive and sometimes synergistic increase in thrombin peak as quantified in the thrombin generation assay has been observed in plasma from hemophilia patients who were on prophylactic treatment with concizumab-mtci with concomitant presence of rFVIII, rFIX or bypassing agents including rFVIIa and aPCC. Depending on concentrations of concizumab-mtci and hemostatic agents, the impact on thrombin peak ranged from being additive with all hemostatic agents to an extra 40% effect with rFVIIa, an extra 33% effect with aPCC, an extra 22% with rFVIII and less than 13% with rFIX.

12.3 Pharmacokinetics

Peak and trough geometric mean plasma concizumab-mtci concentrations at steady state are shown in Table 3. Following a single Alhemo loading dose of 1 mg/kg, the steady state concentrations were reached around Day 4 and remained within a stable exposure range with daily maintenance doses. Concizumab-mtci AUC and Cmax increased with increasing dose in a greater than dose-proportional manner following subcutaneous administration.

Table 3. Steady State Concizumab-mtci Concentrations During 24-hour Dosing Interval at Week 24

Parameters | Hemophilia A and B; without inhibitors; All maintenance doses; N=127a | HAwI and HBwI; All maintenance doses; N=99a
Cmax,ss (ng/mL), geometric mean (CV%); N | 893.4 (144.5%); N=103 | 1167.1 (128%); N=69
Ctrough,ss (ng/mL), geometric mean (CV%); N | 647.3 (178.8%); N=116 | 665.4 (221%); N=94
Cmax / Ctrough ratio, mean (SD); N | 1.5 (0.5); N=103 | 2.2 (5.2); N=69

Abbreviations: Cmax,ss, maximum plasma concentration at steady state; Ctrough,ss, trough plasma concentration at steady state; HAwI, hemophilia A with inhibitors; HBwI, hemophilia B with inhibitors.

a On concizumab-mtci dosing regimen.

Absorption
Concizumab-mtci time to maximum plasma concentration ranged from 8 hours to 99 hours (4.1 days) following a single Alhemo subcutaneous dose of 0.05 to 3 mg/kg in healthy and hemophilia subjects.

Distribution

Concizumab-mtci volume of distribution for a typical 70 kg patient is about 3 L.

Elimination

Concizumab-mtci is cleared via linear and nonlinear mechanisms. Concizumab-mtci exhibited nonlinear pharmacokinetics due to target-mediated drug disposition (TMDD) which occurs when it forms concizumab-mtci/TFPI complex. Once the target becomes saturated, linear pathway (i.e., catabolism) dominates.

Based on population pharmacokinetic analysis, 90% of concizumab-mtci is expected to be eliminated by the end of approximately 4 days after the last dose (time for 50% of drug to be eliminated is approximately 1 day).

Metabolism

Concizumab-mtci is expected to be metabolized into small peptides by catabolic pathways.

Specific Populations
No clinically significant differences in the pharmacokinetics of concizumab-mtci were observed based on age (12 years to 79 years), race (White 64.3%, Asian 25.9%, Black 4.9%), hemophilia type (A and B with or without inhibitors). No dedicated studies have been conducted to evaluate the impact of renal or hepatic impairment. As concizumab-mtci is a monoclonal antibody, there is no expectation for concizumab-mtci exposures to be different in patients with renal or hepatic impairment.

Body weight

The exposure of concizumab-mtci increased with increasing body weight (27 kg to 130.7 kg) [see Use in Specific Populations (8.6)].

12.6 Immunogenicity

The observed incidence of antidrug antibodies is highly dependent on the sensitivity and the specificity of the assay. Differences in assay methods preclude meaningful comparisons of the incidence of antidrug antibodies (ADA) in the studies described below with the incidence of ADA in other studies, including those of concizumab-mtci or of other concizumab products.

During the treatment period in 5 trials with a duration of 11 weeks, ≥76 weeks, ≥76 weeks, ≥56 weeks and ≥56 weeks, 71 out of the 320 treated patients (22.2%) developed anticoncizumab-mtci antibodies. Among the 71 patients who tested positive for ADA, 18 patients (25.4%) developed neutralizing antibodies (NAbs) against concizumab-mtci. In 2 patients (2.8%) who developed NAb against concizumab-mtci, free TFPI levels were restored to baseline indicative of effectiveness likely being compromised. In the remaining 69 patients (97.2%), there was no identified clinically significant effect of the antibodies on pharmacokinetics, pharmacodynamics, safety, or effectiveness of concizumab-mtci.

12.7 Interference of Concizumab-mtci with Laboratory Tests

In vitro studies

No clinically significant interference with standard prothrombin and activated partial thromboplastin time assays or FVIII or FIX activity measurement using clot and chromogenic assays was observed with concizumab-mtci. Further, no clinically relevant interference with assays for inhibitory antibodies to FVIII or FIX (Bethesda assay) was observed with concizumab-mtci.

13 NONCLINICAL TOXICOLOGY

13.1 Carcinogenesis, Mutagenesis, Impairment of Fertility

No long-term animal studies have been conducted to evaluate the carcinogenic potential of concizumab-mtci nor have studies been performed to determine the effects of concizumab-mtci on genotoxicity.

In a 26-week toxicity study in sexually mature male and female cynomolgus monkeys with subcutaneous doses up to 9 mg/kg/day (corresponding to 3400-fold the human exposure, based on AUC0 to 24h), concizumab-mtci did not affect fertility (testicular size, sperm functionality or menstrual cycle duration) and did not cause any changes in the male or female reproductive organs.

13.2 Animal Toxicology and/or Pharmacology

Pharmacology mediated formation of thrombi manifested in cynomolgus monkeys dosed subcutaneously during toxicology studies of 13-weeks (≥ 10 mg/kg/day), 26-weeks (≥ 3 mg/kg/day) and 52-weeks (≥ 1 mg/kg/day) in duration corresponding to ≥ 3732-fold, ≥ 955-fold and ≥ 308-fold, respectively, the human clinical exposure based on AUC0 to 24h in patients with Hemophilia A or B at the MRHD.

In a 28-day drug-drug interaction toxicity study in cynomolgus monkey with daily dosing of 1 mg/kg concizumab-mtci to achieve steady state, three consecutive intravenous doses of up to 1 mg/kg rFVIIa were administered with 2-hour intervals to the concizumab‑mtci dosed animals. No adverse findings were observed at a concizumab-mtci exposure corresponding to 205-fold the human exposure, based on AUC0 to 24h.

14 CLINICAL STUDIES

14.1 Hemophilia A and B with Inhibitors in Patients ≥12 Years of Age (Explorer7)

The efficacy of Alhemo in patients age 12 years and older with hemophilia A and B with inhibitors was evaluated in the explorer7 trial (NCT04083781). The explorer7 trial was a multinational, multicenter, open-label, randomized trial that investigated the safety and efficacy of Alhemo for routine prophylaxis in 91 adults (58 HAwI and 33 HBwI) and 42 adolescents (22 HAwI and 20 HBwI) male patients with hemophilia A or B with inhibitors who have been prescribed, or are in need of, treatment with bypassing agents. Eptacog alfa was the rFVIIa used in explorer7. Patients were excluded if they had a history, current signs or symptoms, or at high risk of thromboembolic events, ongoing or planned immune tolerance induction treatment, in addition to patients with planned major surgery.

Among the 133 patients included in the trial the mean age was 29 years (range: 12 to 79); 42 patients were 12 to <18 years of age, 89 patients were 18 to 64 years of age, and 2 patients were ≥65 years of age, and all were male. Seventy-eight (78) patients were White, 37 patients were Asian, 9 patients were Black or African American, 6 patients had race information unreported, and 3 patients were American Indian or Alaska Native; 6 patients identified as Hispanic or Latino, 122 patients identified as not Hispanic or Latino and 5 patients had ethnicity information unreported.

The trial was comprised of 4 arms, two randomized arms and two nonrandomized arms:

- Arms 1 and 2: 52 patients (27 HAwI, and 25 HBwI), previously treated on-demand, were randomized 1:2 to no prophylaxis (arm 1: on demand treatment with bypassing agents) or Alhemo prophylaxis (arm 2), with stratification by hemophilia type (HAwI, HBwI) and prior 24-week bleeding rate (< 9 or ≥9)
- Arms 3 and 4: 81 additional patients (53 HAwI and 28 HBwI) treated with Alhemo prophylaxis

Treatment with Alhemo included a loading dose of 1 mg/kg by subcutaneous injection on the first day and a once daily dose of 0.2 mg/kg by subcutaneous injection starting on the second day. The dose was individualized to 0.25 mg/kg or 0.15 mg/kg if Alhemo plasma concentration measured once after 4 weeks of treatment was <200 ng/mL or >4000 ng/mL, respectively. Measurement of concizumab-mtci plasma concentration after 4 weeks was used to optimize the daily maintenance dose. In the trial, a total of 108 patients received their individualized dose, 1 patient on 0.15 mg/kg, 79 patients on 0.2 mg/kg and 28 patients on 0.25 mg/kg.

Efficacy was evaluated in hemophilia A and B patients with inhibitors when all patients in arms 1 and 2 had completed at least 24 or at least 32 weeks, respectively, by comparing the number of treated bleeding episodes between Alhemo prophylaxis (arm 2) and no prophylaxis (arm 1). Using a negative binomial model, a ratio of the annualized bleeding rates (ABR) was estimated to 0.14 (p<0.001), corresponding to a reduction in ABR of 86% for subjects on Alhemo prophylaxis compared to no prophylaxis. The estimated mean ABR was 1.7 [95%CI: 1.01; 2.87] for patients on Alhemo prophylaxis (arm 2) and 11.8 [95%CI: 7.03; 19.86] for patients on no prophylaxis (arm 1).

14.2 Hemophilia A and B without Inhibitors in Patients ≥12 Years of Age (Explorer8)

The efficacy of Alhemo in patients 12 years of age and older with hemophilia A and B without inhibitors was established by the explorer8 trial (NCT04082429). The explorer8 trial was an interventional, multinational, multicenter, open-label, randomized trial to investigate efficacy and safety of Alhemo for the prophylaxis treatment of bleeding episodes in 118 adult (67 hemophilia A and 51 hemophilia B) and 38 adolescent (23 hemophilia A and 15 hemophilia B) male patients with hemophilia A or B without inhibitors.

Among the 156 patients included in the trial the mean age was 32 years (range: 12 to 72); 38 patients were 12 to <18 years of age, 114 patients were 18 to 64 years of age, and 4 patients were ≥65 years of age, and all were male. One-hundred-three (103) patients were White, 44 patients were Asian, 4 patients were Black or African American, 3 patients were American Indian or Alaska Native and 2 patients had race information unreported; 12 patients identified as Hispanic or Latino, 143 patients identified as not Hispanic or Latino and 1 patient had ethnicity information unreported.

The trial included two randomized arms:

- Arms 1 and 2: 63 patients (27 hemophilia A and 36 hemophilia B), previously treated on-demand, were randomized 1:2 to no prophylaxis (on demand FVIII/FIX, arm 1) or Alhemo prophylaxis (arm 2), with stratification by hemophilia type (hemophilia A, hemophilia B) and prior 24-week bleeding rate (< 9 or ≥ 9)

Treatment with Alhemo included a loading dose of 1 mg/kg by subcutaneous injection on the first day and a once daily dose of 0.2 mg/kg by subcutaneous injection starting on the second day. The dose was individualized to 0.25 mg/kg or 0.15 mg/kg if Alhemo plasma concentration measured once after 4 weeks of treatment was <200 ng/mL or >4000 ng/mL, respectively. Measurement of concizumab-mtci plasma concentration after 4 weeks was used to optimize the daily maintenance dose. In the trial, a total of 138 patients received their individualized dose, 10 patients on 0.15 mg/kg, 93 patients on 0.2 mg/kg and 35 patients on 0.25 mg/kg.

Efficacy was evaluated separately in hemophilia A patients without inhibitors and in hemophilia B patients without inhibitors when all patients in arms 1 and 2 had completed the main part of the trial (at least 24 or at least 32 weeks, respectively), based on the number of treated bleeding episodes, comparing Alhemo prophylaxis with no prophylaxis.

Using a negative binomial model, a ratio of the annualized bleeding rates (ABR) was estimated to 0.14 (p< 0.001) for patients with hemophilia A, corresponding to a reduction in ABR of 86% for subjects on Alhemo prophylaxis compared to no prophylaxis. Using the same model for patients with hemophilia B, the ratio was estimated to 0.21 (p< 0.001), corresponding to a reduction in ABR of 79% for subjects on Alhemo prophylaxis compared to no prophylaxis. For patients with hemophilia A, the estimated mean ABR was 2.7 [95%CI: 1.63; 4.59] for patients on Alhemo prophylaxis (arm 2) and 19.3 [95%CI: 11.25; 33.03] for patients on no prophylaxis (arm 1). For patients with hemophilia B, the estimated mean ABR was 3.1 [95%CI: 1.91; 5.04] for patients on Alhemo prophylaxis (arm 2) and 14.8 [95%CI: 8.14; 26.86] for patients on no prophylaxis (arm 1).

16 HOW SUPPLIED/STORAGE AND HANDLING

How Supplied

Alhemo (concizumab-mtci) injection is a clear to slightly opalescent, colorless to slightly yellow liquid, that may contain translucent to white particles. Alhemo is available as one single-patient-use prefilled pen per carton in the following presentations (see Table 4):

Table 4. Alhemo Presentations

Presentation | Label | NDC Number
60 mg/1.5 mL (40 mg/mL) | Brown | 0169-2084-15
150 mg/1.5 mL (100 mg/mL) | Gold | 0169-2080-15
300 mg/3 mL (100 mg/mL) | White | 0169-2081-03

Storage and Handling

Before first use: Store in a refrigerator at 36°F to 46°F (2°C to 8°C) in the original carton to protect from light. Do not freeze.

After first use: Store in a refrigerator at 36℉ to 46˚F (2℃ to 8˚C) or at room temperature below 86˚F (30˚C) for up to 28 days. Write the date of first use in the space provided on the carton. Discard the unused portion of the pen 28 days after first opening.

Store Alhemo with the cap on and in the original carton to protect from light. Alhemo should not be stored in direct sunlight, and the Alhemo pen should be kept away from direct heat. Do not freeze or store it close to a cooling element in a refrigerator (the part that cools the refrigerator). Do not use Alhemo if it has been frozen or stored at temperatures above 86˚F (30˚C).

17 PATIENT COUNSELING INFORMATION

Advise the patient to read the FDA-approved patient labeling (Medication Guide and Instructions for Use).

- Thromboembolic events: Inform patients of the signs and symptoms of thromboembolic events, including swelling, warmth, pain, or redness of the skin (and that these could be symptoms of a blood clot in the legs or arms); shortness of breath or severe chest pain (and that these could be symptoms of blood clots in the chest [heart and lungs]).; headache, confusion, difficulty with speech or movement, numbness of the face, eye pain or swelling, or vision problems (and that these could be symptoms of a blood clot in the brain or eyes); or sudden pain in the stomach or lumbar area (and that these could be symptoms of blood clots in the gut or kidneys). Advise patients to contact their healthcare provider for mild reactions and to seek urgent medical attention for moderate to severe reactions [see Warnings and Precautions (5.1)].
- In conditions in which tissue factor is overexpressed (e.g., advanced atherosclerotic disease, crush injury, cancer, or septicemia), there may be a risk of thromboembolic events or disseminated intravascular coagulation (DIC) with Alhemo treatment.
- Hypersensitivity: Inform patients of the early signs of hypersensitivity reactions, including rash, redness, hives, and itching, facial swelling, tightness of the chest, and wheezing as well the signs of an anaphylactic reaction such as itching on large areas of skin; redness and/or swelling of lips, tongue, face, or hands; difficulty swallowing; shortness of breath; wheezing; tightness of the chest; pale and cold skin; fast heartbeat; or dizziness/low blood pressure. Advise patients to discontinue use of Alhemo immediately and contact their healthcare provider if any signs or symptoms occur [see Warnings and Precautions (5.2)].

Advise patients on the importance of adherence to daily dosing and to speak with their healthcare provider before discontinuing treatment with Alhemo as patients who are not adhering to daily dosing or stop treatment with Alhemo may no longer be protected against bleeding.

Advise patients to follow the recommendations regarding proper sharps disposal provided in the FDA-approved Instructions for Use.

Patent Information: http://novonordisk-us.com/products/product-patents.html

Alhemo® is a registered trademark of Novo Nordisk Health Care AG.

NovoFine®, NovoFine® Plus, and Novo Nordisk® are registered trademarks of Novo Nordisk A/S.

For information about Alhemo contact:

Novo Nordisk Inc.

800 Scudders Mill Road

Plainsboro, NJ 08536

1-844-668-6732

Manufactured by:

Novo Nordisk Inc.

800 Scudders Mill Road

Plainsboro, NJ 08536

U.S. License No. 1261

At: Novo Nordisk A/S

Novo Allé 1

2880 Bagsvaerd

Denmark

© 2025 Novo Nordisk

Medication Guide

Alhemo® (al-HEE-mo)

(concizumab-mtci)

injection, for subcutaneous use

What is the most important information I should know about Alhemo?

- It is important to follow the daily dosing schedule of Alhemo to stay protected against bleeding. This is especially important during the first 4 weeks of treatment to make sure a correct maintenance dose is established.Use Alhemo exactly as prescribed by your healthcare provider. Do not stop using Alhemo without talking to your healthcare provider. If you miss doses, or stop using Alhemo, you may no longer be protected against bleeding.
- Your healthcare provider may prescribe factor VIII, factor IX or bypassing agents during treatment with Alhemo. Carefully follow your healthcare provider’s instructions regarding when to use on-demand factor VIII, factor IX or bypassing agents, and the recommended dose and schedule for breakthrough bleeds.

See “How should I use Alhemo?” for more information on how to use Alhemo.

What is Alhemo?

Alhemo is a prescription medicine used for routine prophylaxis to prevent or reduce the frequency of bleeding episodes in adults and children 12 years of age and older with:

- hemophilia A with or without factor VIII inhibitors
- hemophilia B with or without factor IX inhibitors

It is not known if Alhemo is safe and effective in people while receiving ongoing Immune Tolerance Induction (ITI).

It is not known if Alhemo is safe and effective for hemophilia A and B with and without inhibitors in children younger than 12 years of age.

Do not use Alhemo if you are allergic to concizumab-mtci or any of the ingredients in Alhemo. See the end of this Medication Guide for a complete list of ingredients in Alhemo.

Before using Alhemo, tell your healthcare provider about all of your medical conditions, including if you:

- have a planned surgery. Your healthcare provider may stop treatment with Alhemo before your surgery. Talk to your healthcare provider about when to stop using Alhemo and when to start it again if you have a planned surgery.
- are pregnant or plan to become pregnant. It is not known if Alhemo may harm your unborn baby.
Females who are able to become pregnant:
- Your healthcare provider may do a pregnancy test before you start treatment with Alhemo.
- You should use an effective birth control (contraception) during treatment with Alhemo and for 7 weeks after ending treatment. Talk to your healthcare provider about birth control methods that you can use during this time.
- are breastfeeding or plan to breastfeed. It is not known if Alhemo passes into your breast milk. Talk to your healthcare provider about the best way to feed your baby during treatment with Alhemo.

Tell your healthcare provider about all the medicines you take, including prescription and over-the-counter medicines, vitamins, and herbal supplements. Know the medicines you take. Keep a list of them to show your healthcare provider and pharmacist when you get a new medicine.

How should I use Alhemo?

Read the Instructions for Use that comes with Alhemo for information about how to prepare and inject a dose of Alhemo, and how to properly throw away (dispose of) used Alhemo pens and needles.

- Use Alhemo exactly as prescribed by your healthcare provider.
- Your healthcare provider will provide instructions for stopping (discontinuing) your current treatment when switching to Alhemo.
- Inject Alhemo 1 time a day.
- Your healthcare provider should show you or your caregiver how to use Alhemo before you use it for the first time.
- Alhemo is given as an injection under the skin (subcutaneous injection) by you or a caregiver.
- Ask your healthcare provider if you need to use a different injection technique. For example, children and people who are lean may need to inject into a pinched fold of skin to avoid injecting too deep (into the muscle).
- Change (rotate) your injection site with each injection. Do not use the same site for each injection.
- You will inject a larger dose (a loading dose) of Alhemo on your first day of treatment. Then your healthcare provider will prescribe a dose to inject 1 time a day until your maintenance dose is established.
- To determine the right maintenance dose for you, your healthcare provider will do a blood test to check the amount of Alhemo in your blood. Your healthcare provider may do additional blood tests during treatment with Alhemo.
- Your healthcare provider will prescribe your dose based on your weight. If your weight changes, tell your healthcare provider.
- Your healthcare provider will provide information on the treatment of breakthrough bleeding during your treatment with Alhemo.
- Do not share your Alhemo pens and needles with another person, even if the needle has been changed. You may give another person an infection or get an infection from them.
- If you miss a dose of Alhemo during the first 4 weeks of treatment, contact your healthcare provider right away. Your healthcare provider will tell you how much Alhemo to inject.
- If you miss a dose of Alhemo after your daily maintenance dose is established:
- For 1 missed dose, continue your daily maintenance dose.
- For 2 to 6 missed doses, give 2 doses as soon as you remember. Then continue your daily maintenance dose the next day.

- For 7 or more missed doses, contact your healthcare provider right away as you will need to receive a new loading dose before continuing your daily maintenance dose.
- If you are unsure about how much Alhemo to inject, contact your healthcare provider.

What are the possible side effects of Alhemo?

Alhemo may cause serious side effects, including:

- Blood clots (thromboembolic events). Alhemo may cause blood clots to form in blood vessels, such as in your arms, legs, heart, lung, brain, eyes, kidneys, or stomach. You may be at risk for getting blood clots during treatment with Alhemo if you use high or frequent doses of factor products or bypassing agents to treat breakthrough bleeds, or if you have certain conditions.Get medical help right away if you have any signs and symptoms of blood clots, including:

- swelling, warmth, pain, or redness of the skin

- feeling short of breath or severe chest pain

- headache

- confusion

- trouble speaking or moving

- numbness in your face

- eye pain or swelling

- problems with your vision

- sudden pain in your stomach or lower back area

- Allergic reactions. Alhemo can cause allergic reactions, including reactions that can be serious. Stop using Alhemo and tell your healthcare provider right away if you have redness of the skin, rash, hives, itching, and stomach-area (abdominal) pain. Stop using Alhemo and get emergency medical help right away if you develop any signs or symptoms of a severe allergic reaction, including:

- itching on large areas of skin

- redness or swelling of lips, tongue, face, or hands

- trouble swallowing

- shortness of breath

- wheezing

- tightness of the chest

- pale and cold skin

- fast heartbeat

- dizziness due to low blood pressure

The most common side effects of Alhemo include:

- bruising, redness, bleeding, itching, rash, or lump at the injection site

- hives
- headache

These are not all the possible side effects of Alhemo.

Call your doctor for medical advice about side effects. You may report side effects to FDA at 1‑800‑FDA‑1088.

How should I store Alhemo?

- Before first use:
- Store unused Alhemo pens in the refrigerator between 36°F to 46°F (2°C to 8°C).
- After first use:
- Store the Alhemo pen in the refrigerator between 36°F to 46°F (2°C to 8°C) or at room temperature below 86°F (30°C) for up to 28 days.
- Write the date of first use in the space provided on the carton.
- Throw away (discard) the Alhemo pen 28 days after first opening even if some medicine is left in the pen.
- Store Alhemo with the cap on and keep it in the original carton to protect from light.
- Do not store Alhemo in direct sunlight and keep away from direct heat.
- When stored in the refrigerator, do not store the pen directly next to the cooling element (the part that cools the refrigerator).
- Do not freeze Alhemo.
- Do not use Alhemo if it has been frozen or if it has been stored above 86°F (30°C).

Keep Alhemo and all medicine out of the reach of children.

General information about the safe and effective use of Alhemo.

Medicines are sometimes prescribed for purposes other than those listed in a Medication Guide. Do not use Alhemo for a condition for which it was not prescribed. Do not give Alhemo to other people, even if they have the same symptoms that you have. It may harm them. You can ask your pharmacist or healthcare provider for information about Alhemo that is written for health professionals.

What are the ingredients in Alhemo?

Active ingredient: concizumab-mtci

Inactive ingredients: arginine hydrochloride, histidine, phenol, polysorbate 80, sodium chloride, sucrose, and water for injection. Hydrochloric acid and sodium hydroxide may be added for pH adjustment.

Patent Information: http://novonordisk-us.com/products/product-patents.html

Alhemo® is a registered trademark of Novo Nordisk Health Care AG.

For information about Alhemo contact: Novo Nordisk Inc., 800 Scudders Mill Road Plainsboro, NJ 08536.

Manufactured by: Novo Nordisk Inc., 800 Scudders Mill Road, Plainsboro, NJ 08536 U.S. License No. 1261

At: Novo Nordisk A/S, Novo Allé 1, 2880 Bagsværd, Denmark

© 2025 Novo Nordisk

For more information, go to Alhemo.com or call 1-844-668-6732.

This Medication Guide has been approved by the U.S. Food and Drug Administration. Revised:07/2025

Instructions for Use – 1.5 mL (60 mg)

INSTRUCTIONS FOR USE
Alhemo® (al-HEE-mo)

(concizumab-mtci)

injection, for subcutaneous use

60 mg/1.5 mL (40 mg/mL) single-patient-use prefilled pen

This Instructions for Use contains information on how to inject Alhemo. Read and understand these instructions before you use the Alhemo pen. Make sure you have received training from your healthcare provider before you inject with this pen for the first time.

Important information you need to know before injecting Alhemo

- Use Alhemo exactly as prescribed by your healthcare provider.
- Alhemo is supplied as a prefilled pen (called “Alhemo pen” or “pen” in these instructions). It contains 60 milligrams (mg) of Alhemo for subcutaneous injection. The pen contains multiple doses of Alhemo.
- Your Alhemo pen is for single-patient-use only. Do not share your Alhemo pen with other people, even if the needle has been changed. You may give other people a serious infection or get a serious infection from them.
- Your healthcare provider should show you or your caregiver how to use Alhemo before you use it for the first time.
- Ask your healthcare provider if you need to use a different injection technique. For example, children and people who are lean may need to inject into a pinched fold of skin to avoid injecting too deep (into the muscle).
- After 28 days, you must throw away (discard) your pen in an FDA-cleared sharps disposal container even if some medicine is left in the pen.
- The pen can deliver doses from 0.4 mg to 32 mg in one injection. The interval on the dose counter is 0.4 mg. If you need more than 32 mg, you need to inject multiple times. Your healthcare provider will tell you how much Alhemo to inject.

Important information about needles

- Needles can be used for 1 injection only. Always use a new needle for each injection.
- Do not re-use needles as this reduces the risk of contamination, infection, leakage, blocked needles, and incorrect dosing.
- Never share needles with others.
- Alhemo is recommended to be used with NovoFine® and NovoFine® Plus 32G x 4 mm injection needles.
- If you use needles longer than 4 mm, talk to your healthcare provider about how to perform your injection.
- Talk to your healthcare provider or pharmacist for more information about needles for your Alhemo pen.
- Do not use the needle if it is bent or damaged.

Gather the following supplies:

- 1 Alhemo pen

Supplies you will need that are not included in the carton:

- a new needle for each injection.The Alhemo pen is recommended to be used with NovoFine® and NovoFine® Plus needles with a gauge of 32 and length of 4 mm (32G x 4 mm).
- sharps disposal container. See “Throwing away (disposing of) Alhemo pens, needles and needle caps.”
- alcohol swab

Where on my body should I inject my dose?

- You can inject into the skin of:
- your stomach-area (abdomen) at least 2 inches from your belly button (navel)
or
- your upper legs (thigh).
- The gray areas on the picture to the right show the injection sites.
- Change (rotate) your injection site with each injection every day. Do not use the same site for each injection.
- Do not inject into skin that is tender, bruised, red or hard, or areas where there are moles, scars, or stretch marks.

1. Check your Alhemo pen

- Wash your hands with soap and water
Dry them well.
- Check the pen label
Check the name, strength, and colored label to make sure you have the right medicine.
- Check the expiration date
Check the expiration date (EXP) on the pen label to make sure it has not passed (YYYY-MM-DD). If the expiration date has passed, do not use the pen.
- Inspect the medicine
Pull off the pen cap and check that Alhemo in the pen window is almost clear and colorless to slightly yellow. The medicine may contain particles that you can see-through or are white. Do not use the pen if the medicine is discolored.
- If your pen is cold
You can inject Alhemo right from the refrigerator or let it reach room temperature before you inject. You can warm the pen in the palms of your hands. Do not use any other heating sources.

2. Attach a new needle

- Take a new needle and tear off the paper tab.
- Push the needle straight onto your pen. Turn the needle to the right (clockwise) until it is on tight. See Figure A.

- Pull off the outer needle cap. See Figure B.
- Pull off the inner needle cap.See Figure B.
- Throw the needle caps away in a FDA-cleared sharps disposal container.

Note: Always use a new needle for each injection.

3. Prime before each dose. Dial to “0.4” and test the flow before each dose

- A drop of Alhemo may appear at the needle tip, but you should still test the Alhemo flow before each injection to make sure you get the correct dose of Alhemo:
- Turn the dose selector one marking to select 0.4 mg. See Figure C.
- Press the dose button. See Figure D.
- Watch a stream of Alhemo leaving the needle tip. See Figure D.
- If no stream appears, go to “Troubleshooting if no stream appears when testing the flow.”

4. Select your dose

  - Turn the dose selector to select your prescribed dose.
  - You can adjust your dose by turning the dose selector in either direction (forwards or backwards).
  - If you need a larger dose than you can dial, you must inject yourself multiple times to get your full dose. For more information, see Step 6.
  - Each pen contains 60 mg of Alhemo.
  - The pen can deliver doses from 0.4 mg to 32 mg in one injection.

5a. Prepare the injection site

Read Steps 5a and 5b before you start injecting. This is to make sure you get your full dose.

- Select the injection site. See “Where on my body should I inject my dose?”
- Wipe the injection site with an alcohol swab and let the area dry. Do not touch the injection site after cleaning.
- Insert the needle straight into your stomach-area (abdomen) or upper legs (thigh) at a 90-degree angle, as instructed by your healthcare provider.

5b. Inject Alhemo

- Press and hold the dose button down until the dose counter returns to “0”.
- After the dose counter has returned to “0”, count slowly to 6 while the needle is still in your skin.

- Remove the needle from your skin.

The pen clicks during the injection and you might also hear or feel a click when the dose counter returns to “0”.

6. Remove the needle

- Carefully remove the needle from your pen by turning the needle to the left (counterclockwise). Do not touch the pen needle on either side to avoid sticking yourself with the needle.
- Place the needle in an FDA-cleared sharps disposal container right away to reduce the risk of a needle stick. See “Throwing away (disposing of) Alhemo pens, needles and needle caps.”
- Do not put the needle cap back on.

Do you need a larger dose than you can dial?

Repeat Steps 1 to 6 until you have received your full dose. When you have received your full dose go to Step 7.

- Use a new needle for each injection.
- Test the Alhemo flow before each injection.
- Make sure you know how much to inject in each injection to receive your full dose.

Note: Only split your dose if you have been trained or told by your healthcare provider on how to do this.

7. Recap the pen

- Put the pen cap back on your pen to protect Alhemo from light.
- Now your pen is ready for storage until you need it next time. See “Storing Alhemo.”

Troubleshooting if no stream appears when testing the flow (Step 3)

- If no stream appears, repeat Step 3 up to 6 times until you see a stream.
- If still no stream appears, prepare a new needle (Step 2) and test again (Step 3).
- If still no stream appears after attaching a new needle, do not use the pen. Use a new pen or call Novo Nordisk at 1-844-668-6732 for help.

How much Alhemo is left in your pen?

The pen scale shows about how much Alhemo is left in your pen. In the example below, 24 milligrams (mg) is remaining in the pen.

If you want to see more accurately how much Alhemo is left in your pen, turn the dose selector until it stops. The dose pointer will line up with the number of mg left in the pen.

If the dose counter shows 32 mg, at least 32 mg is left in the pen. If the dose counter shows less than 32 mg, the number shown in the dose counter is the number of mg left in your pen. In the example below, the dose counter shows 13.6 mg, so there is 13.6 mg of Alhemo left in the pen.

Storing Alhemo

- Before first use:
- Store unused Alhemo pens in the refrigerator between 36°F to 46°F (2°C to 8°C).
- After first use:
- Store the Alhemo pen in the refrigerator between 36°F to 46°F (2°C to 8°C) or at room temperature no warmer than 86°F (30°C) for up to 28 days.
- Write the date of first use in the space provided on the carton.
- Throw away (discard) the Alhemo pen 28 days after first opening even if some medicine is left in the pen.
- Store Alhemo with the cap on and keep it in the original carton to protect from light.
- Do not store Alhemo in direct sunlight and keep away from direct heat.
- When stored in the refrigerator, do not store the pen directly next to the cooling element (the part that cools the refrigerator).
- Do not freeze Alhemo.
- Do not use Alhemo if it has been frozen or if it has been stored above 86°F (30°C).

Keep Alhemo and all medicine out of the reach of children.

Throwing away (disposing of) Alhemo pens, needles and needle caps

- Put your used pens, needles, and needle caps in an FDA-cleared sharps disposal container right away after use. Do not throw away (dispose of) loose needles and pens in your household trash.
- If you do not have an FDA-cleared sharps disposal container, you may use a household container that is:
- made of heavy-duty plastic,
- can be closed with a tight-fitting, puncture-resistant lid, without sharps being able to come out,
- upright and stable during use,
- leak-resistant, and
- properly labelled to warn of hazardous waste inside the container.
  - When your sharps disposal container is almost full, you will need to follow your community guidelines for the right way to dispose of your sharps disposal container. There may be state or local laws about how you should dispose of used needles and pens. For more information about safe sharps disposal, and for specific information about safe sharps disposal in the state that you live in, go to the FDA’s website at: http://www.fda.gov/safesharpsdisposal.
- Do not dispose of your used sharps disposal container in your household trash unless your community guidelines permit this. Do not recycle your used sharps disposal container.

Scan the QR code below to access the Instructions for Use or visit: www.Alhemo.com

Patent Information: http://novonordisk-us.com/products/product-patents.html

Alhemo® is a registered trademark of Novo Nordisk Health Care AG.

NovoFine®, NovoFine® Plus, and Novo Nordisk® are registered trademarks of Novo Nordisk A/S.

© 2025 Novo Nordisk Health Care AG

For further information contact:

Novo Nordisk Inc.

800 Scudders Mill Road

Plainsboro, NJ 08536, USA

1-844-668-6732

Manufactured by: Novo Nordisk Inc.

800 Scudders Mill Road

Plainsboro, NJ 08536

U.S. License No. 1261

At: Novo Nordisk A/S

Novo Allé 1

2880 Bagsværd

Denmark

This Instructions for Use has been approved by the U.S. Food and Drug Administration.

Revised: 07/2025

Instructions for Use – 1.5 mL (100 mg)

INSTRUCTIONS FOR USE

Alhemo® (al-HEE-mo)

(concizumab-mtci)

injection, for subcutaneous use

150 mg/1.5 mL (100 mg/mL) single-patient-use prefilled pen

This Instructions for Use contains information on how to inject Alhemo. Read and understand these instructions before you use the Alhemo pen. Make sure you have received training from your healthcare provider before you inject with this pen for the first time.

Important information you need to know before injecting Alhemo

- Use Alhemo exactly as prescribed by your healthcare provider.
- Alhemo is supplied as a prefilled pen (called “Alhemo pen” or “pen” in these instructions). It contains 150 milligrams (mg) of Alhemo for subcutaneous injection. The pen contains multiple doses of Alhemo.
- Your Alhemo pen is for single-patient-use only. Do not share your Alhemo pen with other people, even if the needle has been changed. You may give other people a serious infection or get a serious infection from them.
- Your healthcare provider should show you or your caregiver how to use Alhemo before you use it for the first time.
- Ask your healthcare provider if you need to use a different injection technique. For example, children and people who are lean may need to inject into a pinched fold of skin to avoid injecting too deep (into the muscle).
- After 28 days, you must throw away (discard) your pen in an FDA-cleared sharps disposal container even if some medicine is left in the pen.
- The pen can deliver doses from 1 mg to 80 mg in one injection. The interval on the dose counter is 1 mg. If you need more than 80 mg, you need to inject multiple times. Your healthcare provider will tell you how much Alhemo to inject.

Important information about needles

- Needles can be used for 1 injection only. Always use a new needle for each injection.
- Do not re-use needles as this reduces the risk of contamination, infection, leakage, blocked needles, and incorrect dosing.
- Never share needles with others.
- Alhemo is recommended to be used with NovoFine® and NovoFine® Plus 32G x 4 mm injection needles.
- If you use needles longer than 4 mm, talk to your healthcare provider about how to perform your injection.
- Talk to your healthcare provider or pharmacist for more information about needles for your Alhemo pen.
- Do not use the needle if it is bent or damaged.

Gather the following supplies:

- 1 Alhemo pen

Supplies you will need that are not included in the carton:

- a new needle for each injection. The Alhemo pen is recommended to be used with NovoFine® and NovoFine® Plus needles with a gauge of 32 and length of 4 mm (32G x 4 mm).
- sharps disposal container. See “Throwing away (disposing of) Alhemo pens, needles and needle caps.”
- alcohol swab

Where on my body should I inject my dose?

- You can inject into the skin of:
- your stomach-area (abdomen) at least 2 inches from your belly button (navel)
or
- your upper legs (thigh).
- The gray areas on the picture to the right show the injection sites.
- Change (rotate) your injection site with each injection every day. Do not use the same site for each injection.
- Do not inject into skin that is tender, bruised, red or hard, or areas where there are moles, scars, or stretch marks.

1. Check your Alhemo pen

- Wash your hands with soap and water
  Dry them well.
- Check the pen label
Check the name, strength, and colored label to make sure you have the right medicine.
- Check the expiration date
Check the expiration date (EXP) on the pen label to make sure it has not passed (YYYY-MM-DD). If the expiration date has passed, do not use the pen.
- Inspect the medicine
Pull off the pen cap and check that Alhemo in the pen window is almost clear and colorless to slightly yellow. The medicine may contain particles that you can see through or are white. Do not use the pen if the medicine is discolored.
- If your pen is cold
You can inject Alhemo right from the refrigerator or let it reach room temperature before you inject. You can warm the pen in the palms of your hands. Do not use any other heating sources.

2. Attach a new needle

- Take a new needle and tear off the paper tab.
- Push the needle straight onto your pen. Turn the needle to the right (clockwise) until it is
on tight. See Figure A.
- Pull off the outer needle cap. See Figure B.
- Pull off the inner needle cap.See Figure B.
- Throw the needle caps away in a FDA-cleared sharps disposal container.

Note: Always use a new needle for each injection.

3. Prime before each dose. Dial to “1” and test the flow before each dose

- A drop of Alhemo may appear at the needle tip, but you should still test the Alhemo flow before each injection to make sure you get the correct dose of Alhemo:
- Turn the dose selector one marking to select 1 mg. See Figure C.
- Press the dose button. See Figure D.
- Watch a stream of Alhemo leaving the needle tip. See Figure D.
- If no stream appears, go to “Troubleshooting if no stream appears when testing the flow.”

4. Select your dose

- Turn the dose selector to select your prescribed dose.
- You can adjust your dose by turning the dose selector in either direction (forwards or backwards).
- If you need a larger dose than you can dial, you must inject yourself multiple times to get your full dose. For more information, see Step 6.
- Each pen contains 150 mg of Alhemo.
- The pen can deliver doses from 1 mg to 80 mg in one injection.

5a. Prepare the injection site

Read Steps 5a and 5b before you start injecting. This is to make sure you get your full dose.

- Select the injection site. See “Where on my body should I inject my dose?”
- Wipe the injection site with an alcohol swab and let the area dry. Do not touch the injection site after cleaning.
- Insert the needle straight into your stomach-area (abdomen) or upper legs (thigh) at a 90-degree angle, as instructed by your healthcare provider.

5b. Inject Alhemo

- Press and hold the dose button down until the dose counter returns to “0”.
- After the dose counter has returned to “0”, count slowly to 6 while the needle is still in your skin.
- Remove the needle from your skin.

The pen clicks during the injection and you might also hear or feel a click when the dose counter returns to “0”.

6. Remove the needle

- Carefully remove the needle from your pen by turning the needle to the left (counterclockwise). Do not touch the pen needle on either side to avoid sticking yourself with the needle.
- Place the needle in an FDA-cleared sharps disposal container right away to reduce the risk of a needle stick. See “Throwing away (disposing of) Alhemo pens, needles and needle caps.”
- Do not put the needle cap back on.

Do you need a larger dose than you can dial?

Repeat Steps 1 to 6 until you have received your full dose. When you have received your full dose go to Step 7.

- Use a new needle for each injection.
- Test the Alhemo flow before each injection.
- Make sure you know how much to inject in each injection to receive your full dose.
Note: Only split your dose if you have been trained or told by your healthcare provider on how to do this.

7. Recap the pen

- Put the pen cap back on your pen to protect Alhemo from light.
- Now your pen is ready for storage until you need it next time. See “Storing Alhemo.”

Troubleshooting if no stream appears when testing the flow (Step 3)

- If no stream appears, repeat Step 3 up to 6 times until you see a stream.
- If still no stream appears, prepare a new needle (Step 2) and test again (Step 3).
- If still no stream appears after attaching a new needle, do not use the pen. Use a new pen or call Novo Nordisk at 1-844-668-6732 for help.

How much Alhemo is left in your pen?

The pen scale shows about how much Alhemo is left in your pen. In the example below, 60 milligrams (mg) is remaining in the pen.

If you want to see more accurately how much Alhemo is left in your pen, turn the dose selector until it stops. The dose pointer will line up with the number of mg left in the pen.

If the dose counter shows 80 mg, at least 80 mg is left in the pen. If the dose counter shows less than 80 mg, the number shown in the dose counter is the number of mg left in your pen. In the example below, the dose counter shows 34 mg, so there is 34 mg of Alhemo left in the pen.

Storing Alhemo

- Before first use:
- Store unused Alhemo pens in the refrigerator between 36°F to 46°F (2°C to 8°C).
- After first use:
- Store the Alhemo pen in the refrigerator between 36°F to 46°F (2°C to 8°C) or at room temperature no warmer than 86°F (30°C) for up to 28 days.
- Write the date of first use in the space provided on the carton.
- Throw away (discard) the Alhemo pen 28 days after first opening even if some medicine is left in the pen.
- Store Alhemo with the cap on and keep it in the original carton to protect from light.
- Do not store Alhemo in direct sunlight and keep away from direct heat.
- When stored in the refrigerator, do not store the pen directly next to the cooling element (the part that cools the refrigerator).
- Do not freeze Alhemo.
- Do not use Alhemo if it has been frozen or if it has been stored above 86°F (30°C).

Keep Alhemo and all medicine out of the reach of children.

Throwing away (disposing of) Alhemo pens, needles and needle caps

- Put your used pens, needles, and needle caps in an FDA-cleared sharps disposal container right away after use. Do not throw away (dispose of) loose needles and pens in your household trash.
- If you do not have an FDA-cleared sharps disposal container, you may use a household container that is:
- made of heavy-duty plastic,
- can be closed with a tight-fitting, puncture-resistant lid, without sharps being able to come out,
- upright and stable during use,
- leak-resistant, and
- properly labelled to warn of hazardous waste inside the container.
  - When your sharps disposal container is almost full, you will need to follow your community guidelines for the right way to dispose of your sharps disposal container. There may be state or local laws about how you should dispose of used needles and pens. For more information about safe sharps disposal, and for specific information about safe sharps disposal in the state that you live in, go to the FDA’s website at: http://www.fda.gov/safesharpsdisposal.
- Do not dispose of your used sharps disposal container in your household trash unless your community guidelines permit this. Do not recycle your used sharps disposal container.

Scan the QR code below to access the Instructions for Use or visit: www.Alhemo.com

Patent Information: http://novonordisk-us.com/products/product-patents.html

Alhemo® is a registered trademark of Novo Nordisk Health Care AG.

NovoFine®, NovoFine® Plus, and Novo Nordisk® are registered trademarks of Novo Nordisk A/S.

© 2025 Novo Nordisk Health Care AG

For further information contact:

Novo Nordisk Inc.

800 Scudders Mill Road

Plainsboro, NJ 08536, USA

1-844-668-6732

Manufactured by:

Novo Nordisk Inc.

800 Scudders Mill Road

Plainsboro, NJ 08536

U.S. License No. 1261

At: Novo Nordisk A/S

Novo Allé 1

2880 Bagsvaerd

Denmark

This Instructions for Use has been approved by the U.S. Food and Drug Administration.

Revised: 07/2025

Instructions for Use – 3.0 mL (300 mg)

INSTRUCTIONS FOR USE

Alhemo® (al-HEE-mo)

(concizumab-mtci)

injection, for subcutaneous use

300 mg/3 mL (100 mg/mL) single-patient-use prefilled pen

This Instructions for Use contains information on how to inject Alhemo. Read and understand these instructions before you use the Alhemo pen. Make sure you have received training from your healthcare provider before you inject with this pen for the first time.

Important information you need to know before injecting Alhemo

- Use Alhemo exactly as prescribed by your healthcare provider.
- Alhemo is supplied as a prefilled pen (called “Alhemo pen” or “pen” in these instructions). It contains 300 milligrams (mg) of Alhemo for subcutaneous injection. The pen contains multiple doses of Alhemo.
- Your Alhemo pen is for single-patient-use only. Do not share your Alhemo pen with other people, even if the needle has been changed. You may give other people a serious infection or get a serious infection from them.
- Your healthcare provider should show you or your caregiver how to use Alhemo before you use it for the first time.
- Ask your healthcare provider if you need to use a different injection technique. For example, children and people who are lean may need to inject into a pinched fold of skin to avoid injecting too deep (into the muscle).
- After 28 days, you must throw away (discard) your pen in an FDA-cleared sharps disposal container even if some medicine is left in the pen.
- The pen can deliver doses from 1 mg to 80 mg in one injection. The interval on the dose counter is 1 mg. If you need more than 80 mg, you need to inject multiple times. Your healthcare provider will tell you how much Alhemo to inject.

Important information about needles

- Needles can be used for 1 injection only. Always use a new needle for each injection.
- Do not re-use needles as this reduces the risk of contamination, infection, leakage, blocked needles, and incorrect dosing.
- Never share needles with others.
- Alhemo is recommended to be used with NovoFine® and NovoFine® Plus 32G x 4 mm injection needles.
- If you use needles longer than 4 mm, talk to your healthcare provider about how to perform your injection.
- Talk to your healthcare provider or pharmacist for more information about needles for your Alhemo pen.
- Do not use the needle if it is bent or damaged.

Gather the following supplies:

- 1 Alhemo pen

Supplies you will need that are not included in the carton:

- a new needle for each injection. The Alhemo pen is recommended to be used with NovoFine® and NovoFine® Plus needles with a gauge of 32 and length of 4 mm (32G x 4 mm).
- sharps disposal container. See “Throwing away (disposing of) Alhemo pens, needles and needle caps.”
- alcohol swab

Where on my body should I inject my dose?

- You can inject into the skin of:
- your stomach-area (abdomen) at least 2 inches from your belly button (navel)
or
- your upper legs (thigh).
- The gray areas on the picture to the right show the injection sites.
- Change (rotate) your injection site with each injection every day. Do not use the same site for each injection.
- Do not inject into skin that is tender, bruised, red or hard, or areas where there are moles, scars, or stretch marks.

1. Check your Alhemo pen

- Wash your hands with soap and water
Dry them well.
- Check the pen label
Check the name, strength, and colored label to make sure you have the right medicine.
- Check the expiration date
Check the expiration date (EXP) on the pen label to make sure it has not passed (YYYY-MM-DD). If the expiration date has passed, do not use the pen.
- Inspect the medicine
Pull off the pen cap and check that Alhemo in the pen window is almost clear and colorless to slightly yellow. The medicine may contain particles that you can see through or are white. Do not use the pen if the medicine is discolored.
- If your pen is cold
You can inject Alhemo right from the refrigerator or let it reach room temperature before you inject. You can warm the pen in the palms of your hands. Do not use any other heating sources.

2. Attach a new needle

- Take a new needle and tear off the paper tab.
- Push the needle straight onto your pen. Turn the needle to the right (clockwise) until it is
on tight. See Figure A.
- Pull off the outer needle cap. See Figure B.
- Pull off the inner needle cap.See Figure B.
- Throw the needle caps away in a FDA-cleared sharps disposal container.

Note: Always use a new needle for each injection.

3. Prime before each dose. Dial to “1” and test the flow before each dose

- A drop of Alhemo may appear at the needle tip, but you should still test the Alhemo flow before each injection to make sure you get the correct dose of Alhemo:
- Turn the dose selector one marking to select 1 mg. See Figure C.
- Press the dose button. See Figure D.
- Watch a stream of Alhemo leaving the needle tip. See Figure D.
- If no stream appears, go to “Troubleshooting if no stream appears when testing the flow.”

4. Select your dose

- Turn the dose selector to select your prescribed dose.
- You can adjust your dose by turning the dose selector in either direction (forwards or backwards).
- If you need a larger dose than you can dial, you must inject yourself multiple times to get your full dose. For more information, see Step 6.
- Each pen contains 300 mg of Alhemo.
- The pen can deliver doses from 1 mg to 80 mg in one injection.

5a. Prepare the injection site

Read Steps 5a and 5b before you start injecting. This is to make sure you get your full dose.

- Select the injection site. See “Where on my body should I inject my dose?”
- Wipe the injection site with an alcohol swab and let the area dry. Do not touch the injection site after cleaning.
- Insert the needle straight into your stomach-area (abdomen) or upper legs (thigh) at a 90-degree angle, as instructed by your healthcare provider.

5b. Inject Alhemo

- Press and hold the dose button down until the dose counter returns to “0”.
- After the dose counter has returned to “0”, count slowly to 6 while the needle is still in your skin.

- Remove the needle from your skin.

The pen clicks during the injection and you might also hear or feel a click when the dose counter returns to “0”.

6. Remove the needle

- Carefully remove the needle from your pen by turning the needle to the left (counterclockwise). Do not touch the pen needle on either side to avoid sticking yourself with the needle.
- Place the needle in an FDA-cleared sharps disposal container right away to reduce the risk of a needle stick. See “Throwing away (disposing of) Alhemo pens, needles and needle caps.”
- Do not put the needle cap back on.

Do you need a larger dose than you can dial?

Repeat Steps 1 to 6 until you have received your full dose. When you have received your full dose go to Step 7.

- Use a new needle for each injection.
- Test the Alhemo flow before each injection.
- Make sure you know how much to inject in each injection to receive your full dose.
Note: Only split your dose if you have been trained or told by your healthcare provider on how to do this.

7. Recap the pen

- Put the pen cap back on your pen to protect Alhemo from light.
- Now your pen is ready for storage until you need it next time. See “Storing Alhemo.”

Troubleshooting if no stream appears when testing the flow (Step 3)

- If no stream appears, repeat Step 3 up to 6 times until you see a stream.
- If still no stream appears, prepare a new needle (Step 2) and test again (Step 3).
- If still no stream appears after attaching a new needle, do not use the pen. Use a new pen or call Novo Nordisk at 1-844-668-6732 for help.

How much Alhemo is left in your pen?

The pen scale shows about how much Alhemo is left in your pen. In the example below, 200 milligrams (mg) is remaining in the pen.

If you want to see more accurately how much Alhemo is left in your pen, turn the dose selector until it stops. The dose pointer will line up with the number of mg left in the pen.

If the dose counter shows 80 mg, at least 80 mg is left in the pen. If the dose counter shows less than 80 mg, the number shown in the dose counter is the number of mg left in your pen. In the example below, the dose counter shows 34 mg, so there is 34 mg of Alhemo left in the pen.

Storing Alhemo

- Before first use:
- Store unused Alhemo pens in the refrigerator between 36°F to 46°F (2°C to 8°C).
- After first use:
- Store the Alhemo pen in the refrigerator between 36°F to 46°F (2°C to 8°C) or at room temperature no warmer than 86°F (30°C) for up to 28 days.
- Write the date of first use in the space provided on the carton.
- Throw away (discard) the Alhemo pen 28 days after first opening even if some medicine is left in the pen.
- Store Alhemo with the cap on and keep it in the original carton to protect from light.
- Do not store Alhemo in direct sunlight and keep away from direct heat.
- When stored in the refrigerator, do not store the pen directly next to the cooling element (the part that cools the refrigerator).
- Do not freeze Alhemo.
- Do not use Alhemo if it has been frozen or if it has been stored above 86°F (30°C).

Keep Alhemo and all medicine out of the reach of children.

Throwing away (disposing of) Alhemo pens, needles and needle caps

- Put your used pens, needles, and needle caps in an FDA-cleared sharps disposal container right away after use. Do not throw away (dispose of) loose needles and pens in your household trash.
- If you do not have an FDA-cleared sharps disposal container, you may use a household container that is:
- made of heavy-duty plastic,
- can be closed with a tight-fitting, puncture-resistant lid, without sharps being able to come out,
- upright and stable during use,
- leak-resistant, and
- properly labelled to warn of hazardous waste inside the container.
- When your sharps disposal container is almost full, you will need to follow your community guidelines for the right way to dispose of your sharps disposal container. There may be state or local laws about how you should dispose of used needles and pens. For more information about safe sharps disposal, and for specific information about safe sharps disposal in the state that you live in, go to the FDA’s website at: http://www.fda.gov/safesharpsdisposal.
- Do not dispose of your used sharps disposal container in your household trash unless your community guidelines permit this. Do not recycle your used sharps disposal container.

Scan the QR code below to access the Instructions for Use or visit: www.Alhemo.com

Patent Information: http://novonordisk-us.com/products/product-patents.html

Alhemo® is a registered trademark of Novo Nordisk Health Care AG.

NovoFine®, NovoFine® Plus, and Novo Nordisk® are registered trademarks of Novo Nordisk A/S.

© 2025 Novo Nordisk Health Care AG

For further information contact:

Novo Nordisk Inc.

800 Scudders Mill Road

Plainsboro, NJ 08536, USA

1-844-668-6732

Manufactured by:

Novo Nordisk Inc.

800 Scudders Mill Road

Plainsboro, NJ 08536

U.S. License No. 1261

At: Novo Nordisk A/S

Novo Allé 1

2880 Bagsvaerd

Denmark

This Instructions for Use has been approved by the U.S. Food and Drug Administration.

Revised: 07/2025

PACKAGE/LABEL PRINCIPAL DISPLAY PANEL – 60 mg

NDC 0169-2084-15 List: 208415
Alhemo®
(concizumab-mtci) injection

60 mg/1.5 mL (40 mg/mL)

For subcutaneous use only

1x1.5 mL single-patient use prefilled pen

Dials in 0.4 mg increments and contains

60 mg total

Rx only

ATTENTION: Dispense the enclosed Medication Guide to each patient.

PACKAGE/LABEL PRINCIPAL DISPLAY PANEL – 150 mg

NDC 0169-2080-15 List: 208015
Alhemo®
(concizumab-mtci) injection

150 mg/1.5 mL (100 mg/mL)

For subcutaneous use only

1x1.5 mL single-patient use prefilled pen

Dials in 1 mg increments and contains 150 mg total

Rx only

ATTENTION: Dispense the enclosed Medication Guide to each patient.

PACKAGE/LABEL PRINCIPAL DISPLAY PANEL – 300 mg

NDC 0169-2081-03 List : 208103
Alhemo®
(concizumab-mtci) injection

300 mg/3 mL (100 mg/mL)

Prefilled Pen

For subcutaneous use only

1x3 mL single-patient use prefilled pen

Dials in 1 mg increments and contains

300 mg total

Rx only

ATTENTION: Dispense the enclosed Medication Guide to each patient.